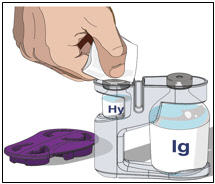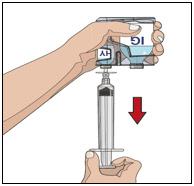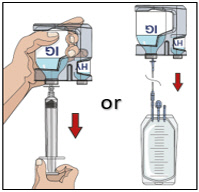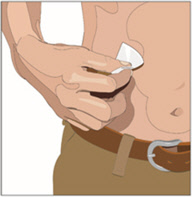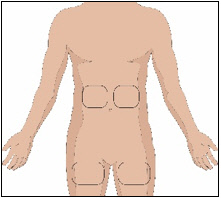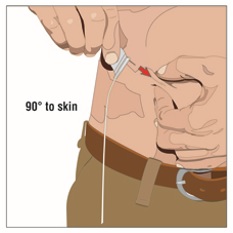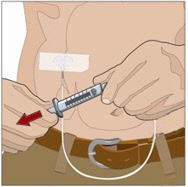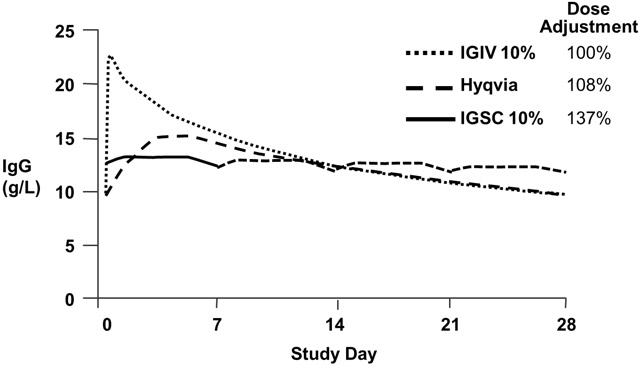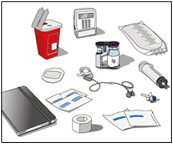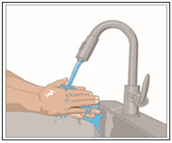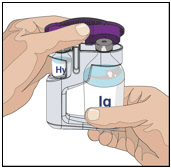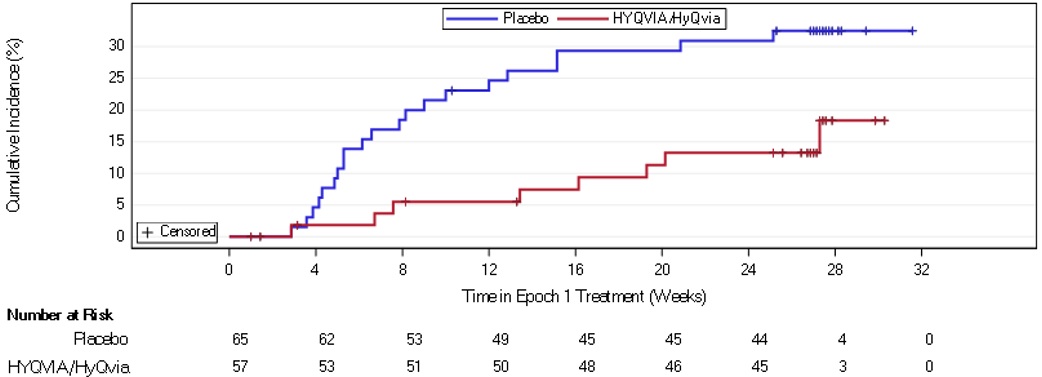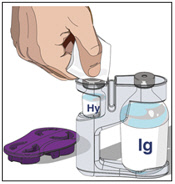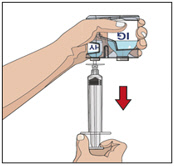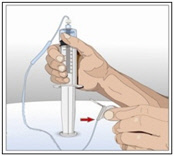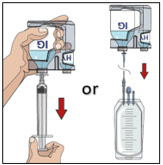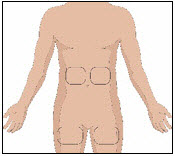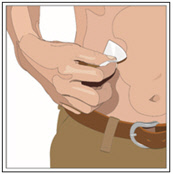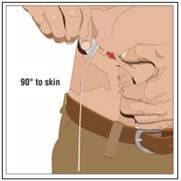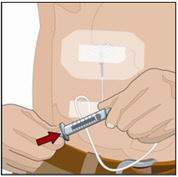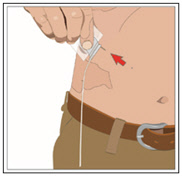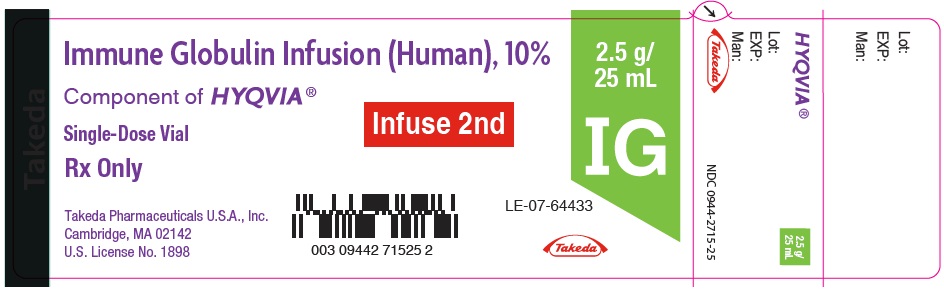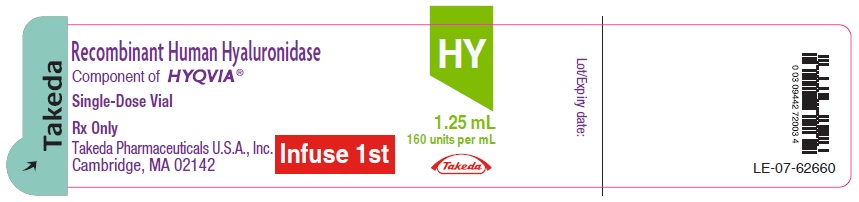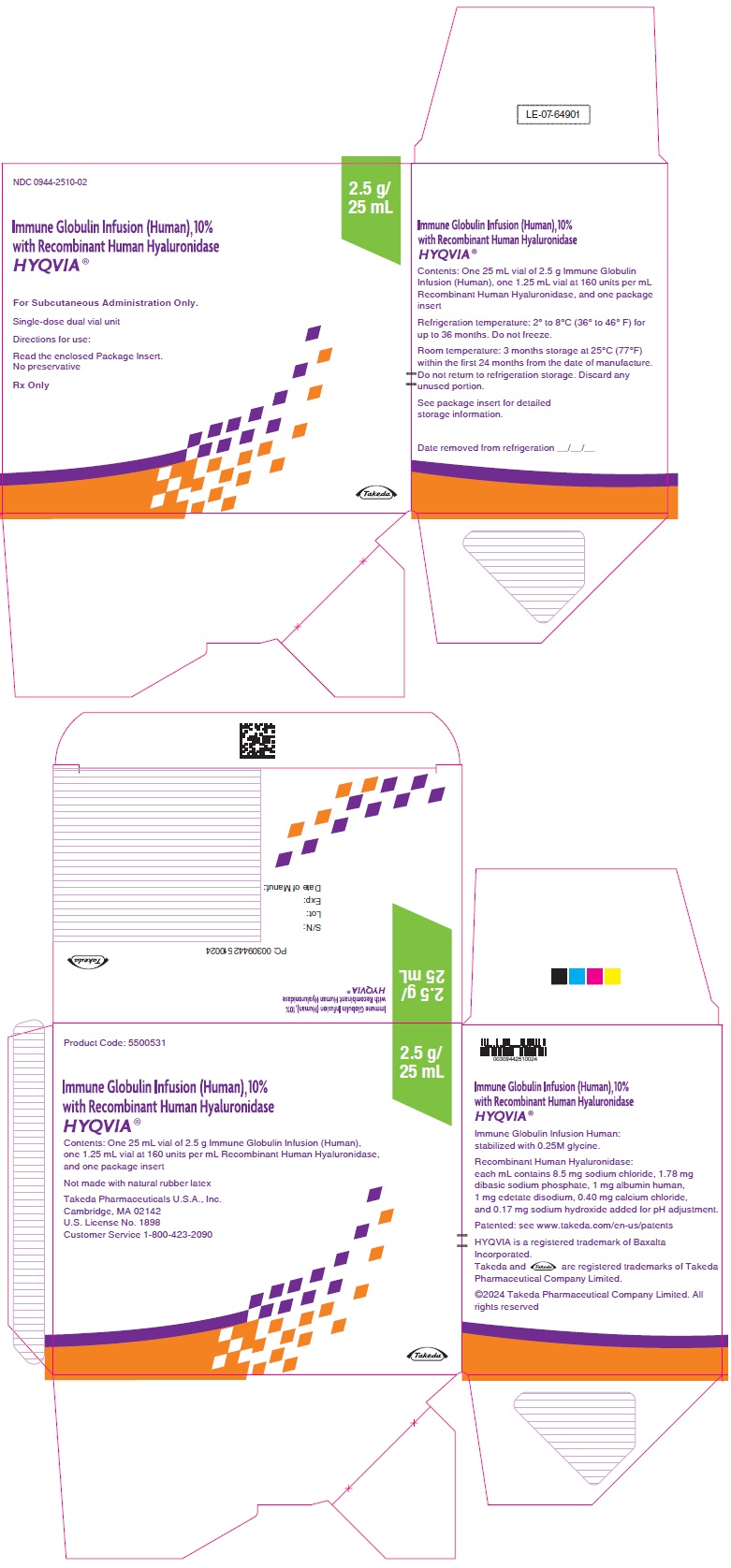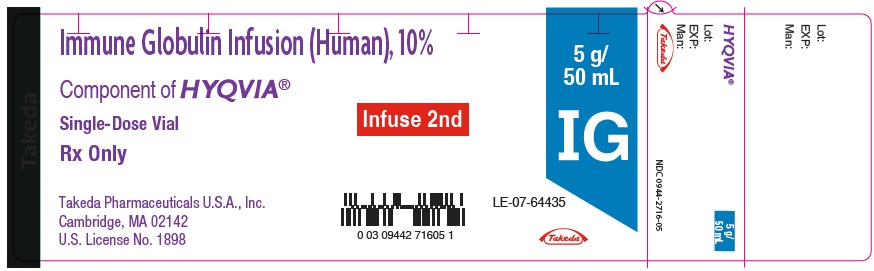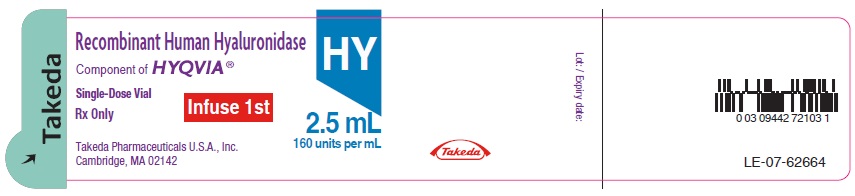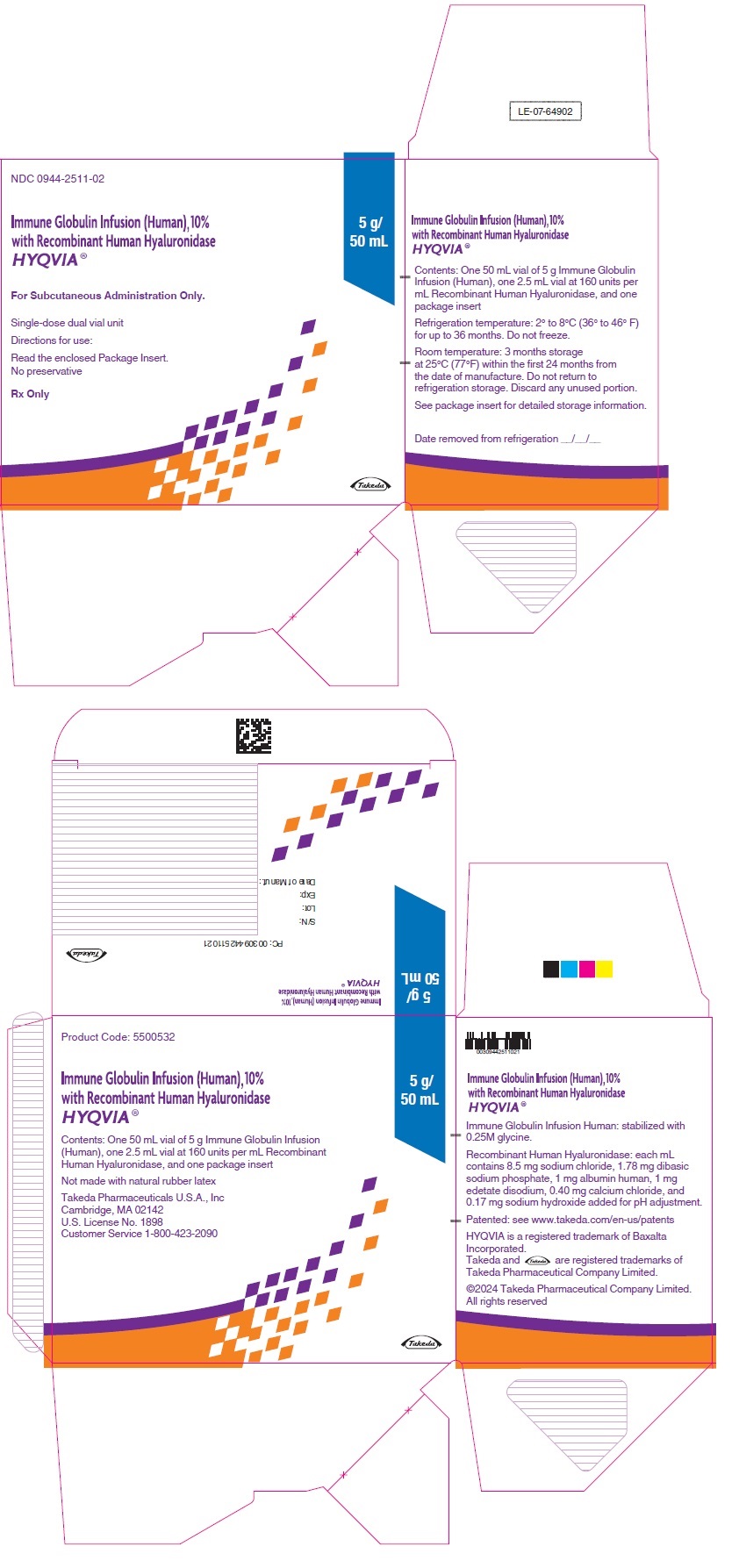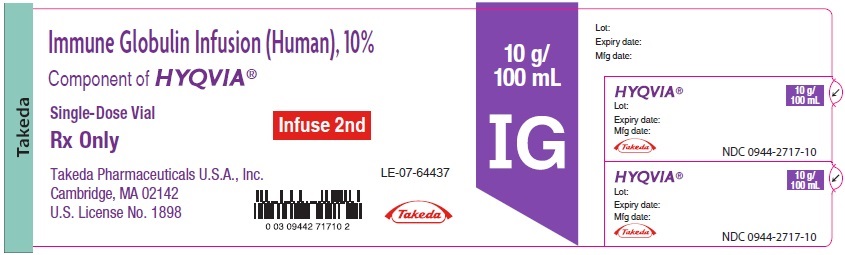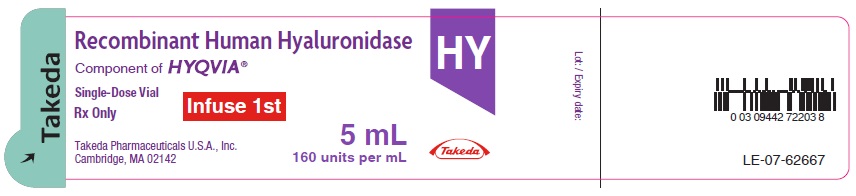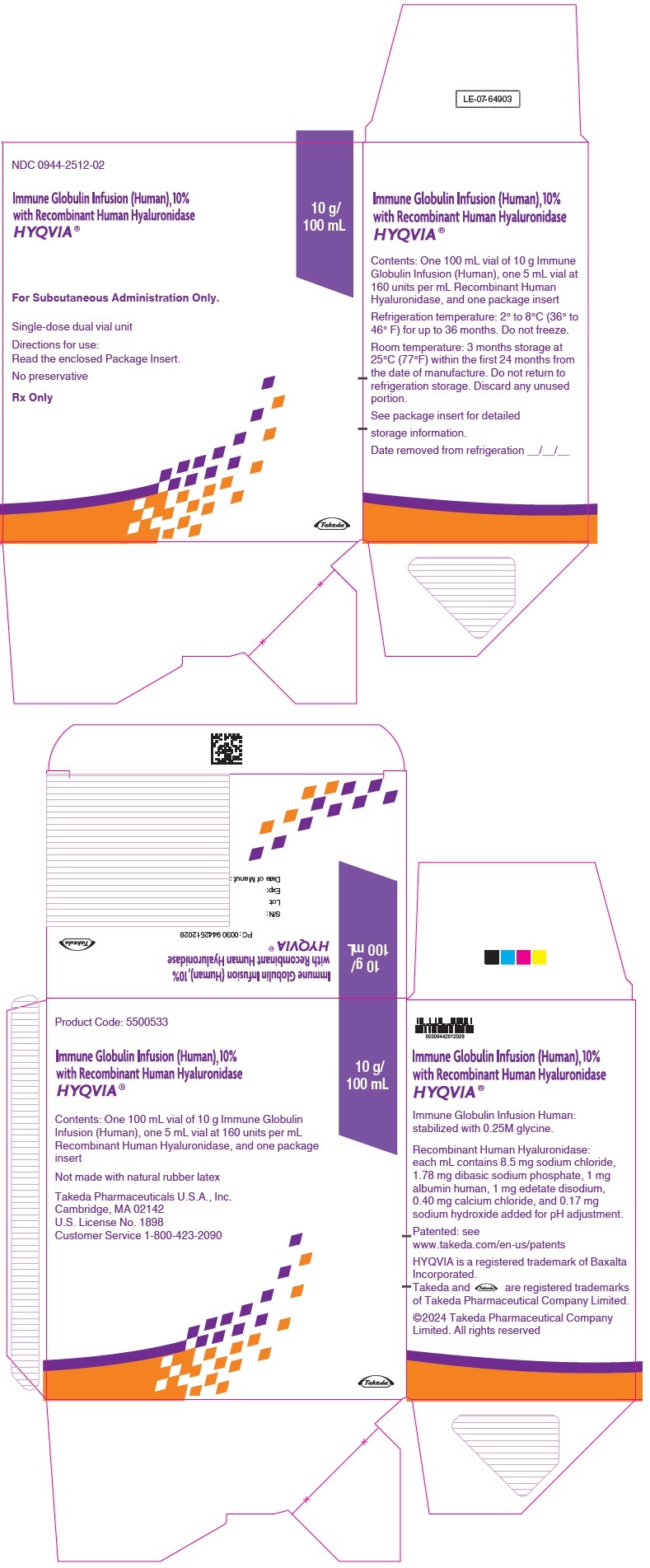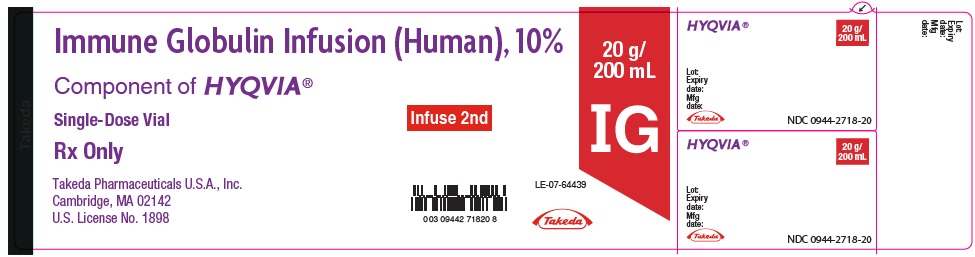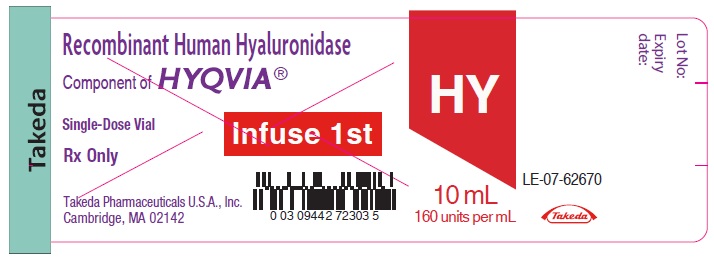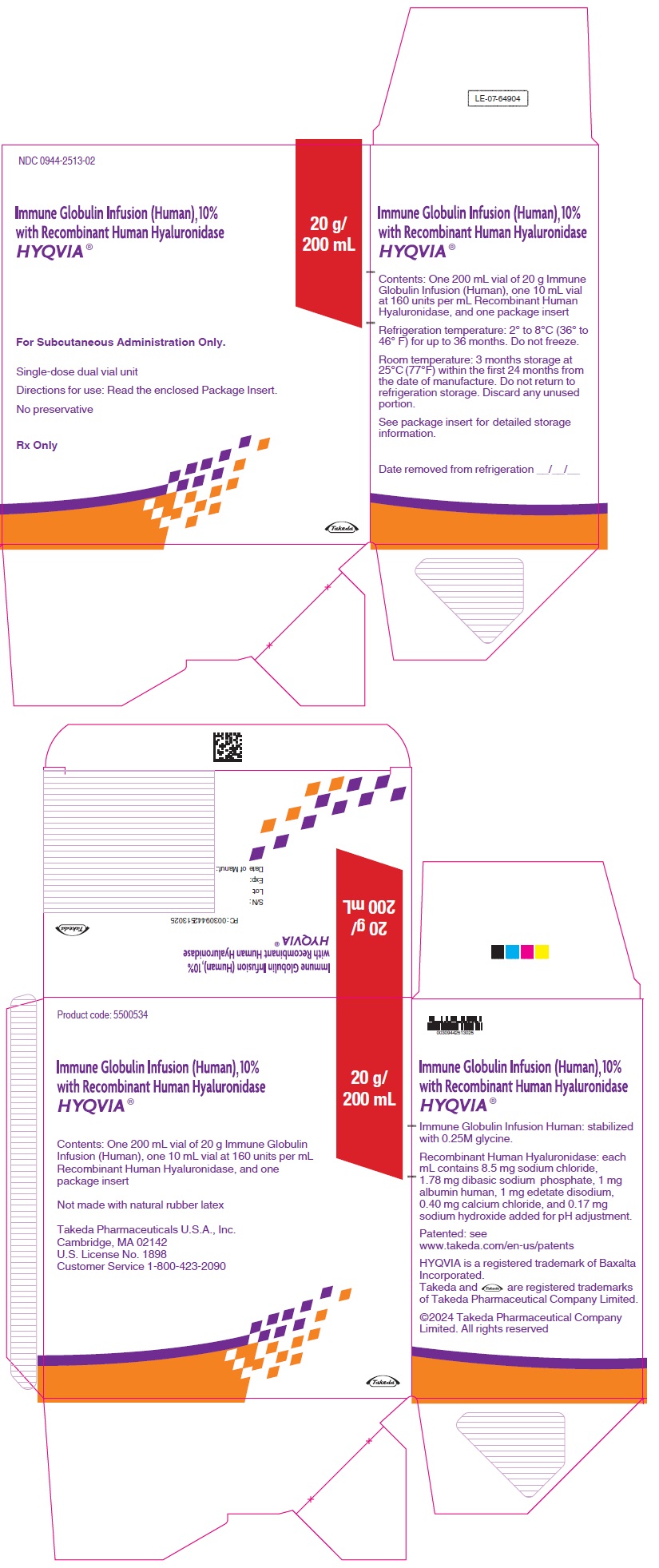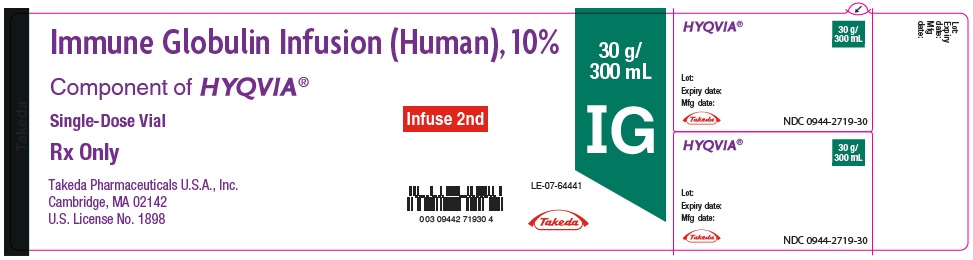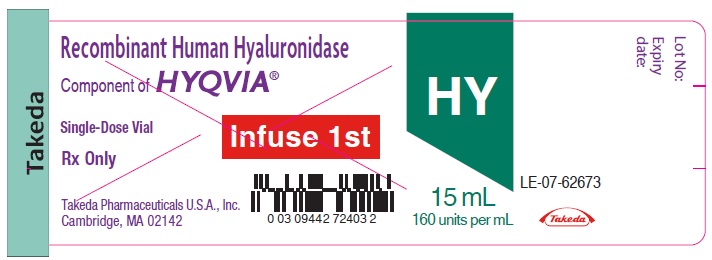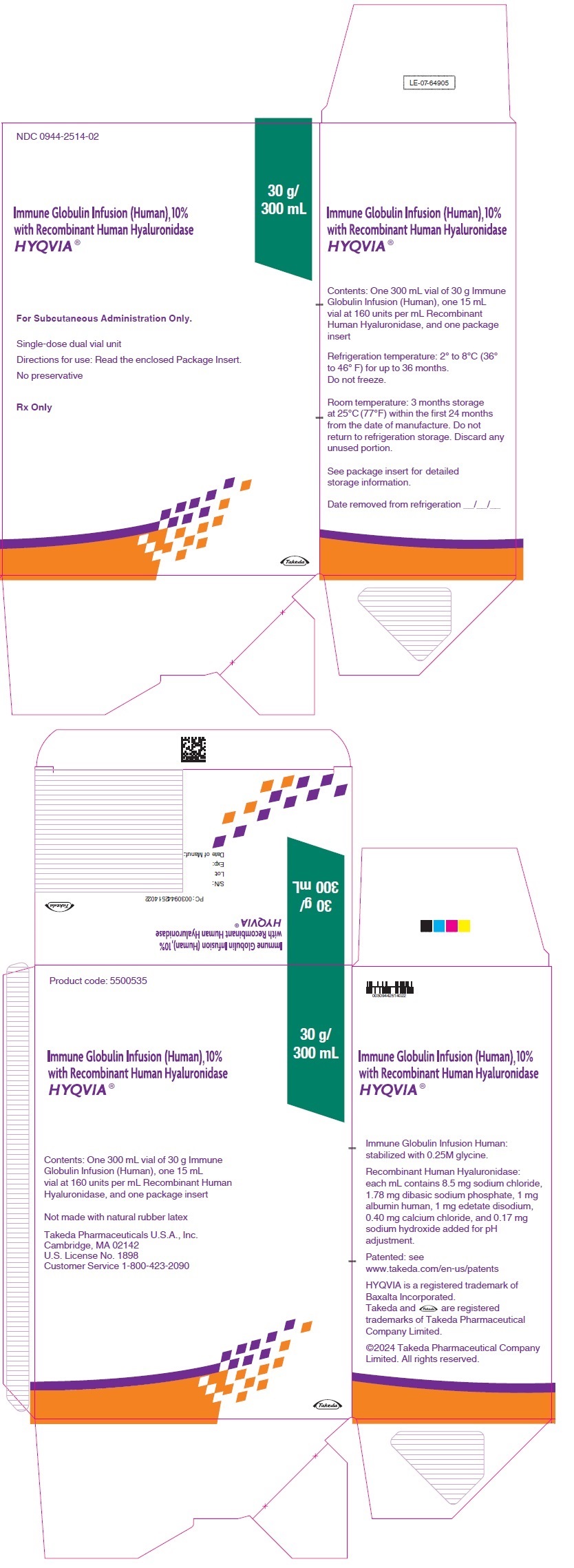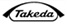 DRUG LABEL: HYQVIA
NDC: 0944-2510 | Form: KIT | Route: SUBCUTANEOUS
Manufacturer: Takeda Pharmaceuticals America, Inc.
Category: other | Type: PLASMA DERIVATIVE
Date: 20260204

ACTIVE INGREDIENTS: HUMAN IMMUNOGLOBULIN G 100 mg/1 mL; HYALURONIDASE (HUMAN RECOMBINANT) 160 [USP'U]/1 mL
INACTIVE INGREDIENTS: GLYCINE; SODIUM CHLORIDE; SODIUM PHOSPHATE; ALBUMIN HUMAN; EDETATE DISODIUM; CALCIUM CHLORIDE; SODIUM HYDROXIDE

HIGHLIGHTS OF PRESCRIBING INFORMATION

These highlights do not include all the information needed to use HYQVIA® safely and effectively. See full prescribing information for HYQVIA.
HYQVIA® [Immune Globulin Infusion (Human), 10% with Recombinant Human Hyaluronidase] Solution, for subcutaneous administration
Initial U.S. Approval: 2014

WARNING: THROMBOSIS

See full prescribing information for complete boxed warning.

- Thrombosis may occur with immune globulin products, including HYQVIA. Risk factors may include advanced age, prolonged immobilization, hypercoagulable conditions, history of venous or arterial thrombosis, use of estrogens, indwelling vascular catheters, hyperviscosity and cardiovascular risk factors. (5.2)
- For patients at risk of thrombosis, administer HYQVIA at the minimum dose and infusion rate practicable. Ensure adequate hydration in patients before administration. (5.2)
- Monitor for signs and symptoms of thrombosis and assess blood viscosity in patients at risk of hyperviscosity. (5.2)

RECENT MAJOR CHANGES

• Dosage and Administration, Administration (2.3) | 7/2025

1 INDICATIONS AND USAGE

HYQVIA is an Immune Globulin Infusion (Human), 10% with a Recombinant Human Hyaluronidase (rHuPH20) indicated for the treatment of

- Primary Immunodeficiency (PI) in adults and pediatric patients two years of age and older. (1.1)
- Maintenance therapy in adults with chronic inflammatory demyelinating polyneuropathy (CIDP) (1.2)

2 DOSAGE AND ADMINISTRATION

For subcutaneous use only

The recommended rHuPH20 dose is 80 U/g Immune globulin G (IgG), which corresponds to 0.5 mL rHuPH20 solution per 10 mL Immune Globulin Infusion (Human), 10% solution for both indications. (2.1)

PI (2.1)

Initiation of Treatment with HYQVIA

- Administer the first dose approximately one week after the last infusion of their previous treatment. (2.1)
- Increase the dose and frequency from a 1-week dose to a 3-or 4-week dose. (2.1)

Switching from Immune Globulin Intravenous (Human) [IGIV] treatment:

- Use same dose and frequency as previous intravenous treatment after the initial ramp-up. (2.1)

Naïve to Immune Globulin Subcutaneous (Human) [IGSC] treatment or switching from IGSC treatment:

- 300 to 600 mg/kg at 3 to 4-week intervals, after initial ramp-up. (2.1)

CIDP (2.1)

Switching from Immune Globulin Intravenous (Human) [IGIV] treatment:

- Patient must be on stable doses of IGIV. (2.1)
- The starting dose and dosing frequency of HYQVIA is the same as the patient’s previous IGIV treatment. The typical dosing interval range in the clinical trial for HYQVIA was 2 to 4 weeks. (2.1)

3 DOSAGE FORMS AND STRENGTHS

HYQVIA is a dual vial unit containing 100 mg/mL of Immune Globulin Infusion (Human), 10% and 160 U/mL of rHuPH20. (3)

HYQVIA is available in the following vial volumes: 25 mL, 50 mL, 100 mL, 200 mL, and 300 mL. (3)

4 CONTRAINDICATIONS

- History of anaphylactic or severe systemic hypersensitivity reactions to Immune Globulin (Human). (4)
- IgA deficient patients with antibodies against IgA and a history of hypersensitivity. (4)
- Known systemic hypersensitivity to hyaluronidase including Recombinant Human Hyaluronidase of HYQVIA. (4)
- Known systemic hypersensitivity to human albumin (in the hyaluronidase solution). (4)

5 WARNINGS AND PRECAUTIONS

- IgA-deficient patients with anti-IgA antibodies are at greater risk of severe hypersensitivity and anaphylactic reactions. (5.1)
- Thrombosis may occur following treatment with immune globulin products including HYQVIA. (5.2)
- Antibodies to rHuPH20 can develop. The potential exists for such antibodies to cross-react with endogenous Hyaluronidase (PH20) which is known to be expressed in the adult male testes, epididymis, and sperm. It is unknown whether these antibodies may interfere with fertilization in humans. The clinical significance of these antibodies is not known. (5.3)
- Aseptic Meningitis Syndrome (AMS) may occur. Discontinue treatment if AMS symptoms appear. (5.4)
- Acute intravascular hemolysis may occur. Monitor for clinical signs and symptoms of hemolysis and hemolytic anemia. (5.5)
- Infusion into or around an infected area can spread a localized infection. (5.7)
- Monitor for pulmonary adverse reactions (transfusion-related acute lung injury [TRALI]). (5.8)
- May carry a risk of transmitting infectious agents, e.g., viruses, the variant Creutzfeldt-Jakob disease (vCJD) agent and, theoretically, the Creutzfeldt-Jakob disease (CJD) agent. (5.9)

6 ADVERSE REACTIONS

PI: The most common adverse reactions observed in >5% of patients were local reactions, headache, antibody formation against rHuPH20, fatigue, nausea, pyrexia, and vomiting. (6)

CIDP: The most common adverse reactions observed in >5% of patients were local reactions, headache, pyrexia, nausea, fatigue, erythema, pruritus, increased lipase, abdominal pain, back pain, and pain in extremity. (6)

To report SUSPECTED ADVERSE REACTIONS, contact Takeda Pharmaceuticals U.S.A., Inc. at 1-877-TAKEDA-7 (1-877-825-3327) or FDA at 1-800-FDA-1088 or www.fda.gov/medwatch.

7 DRUG INTERACTIONS

Passive transfer of antibodies may transiently interfere with the immune responses to live virus vaccines, such as measles, mumps, and rubella. (7)

8 USE IN SPECIFIC POPULATIONS

Geriatric: In patients over age 65 or in any patient at risk of developing renal insufficiency, do not exceed the recommended dose, and consider infusing HYQVIA at lower, more frequent doses. (8.5)

FULL PRESCRIBING INFORMATION

WARNING: THROMBOSIS

- Thrombosis may occur with immune globulin products, including HYQVIA. Risk factors may include advanced age, prolonged immobilization, hypercoagulable conditions, history of venous or arterial thrombosis, use of estrogens, indwelling vascular catheters, hyperviscosity and cardiovascular risk factors. Thrombosis may occur in the absence of known risk factors. [see Warnings and Precautions (5.2)]
- For patients at risk of thrombosis, administer HYQVIA at the minimum dose and infusion rate practicable. Ensure adequate hydration in patients before administration. [see Warnings and Precautions (5.2)]
- Monitor for signs and symptoms of thrombosis and assess blood viscosity in patients at risk of hyperviscosity. [see Warnings and Precautions (5.2)]

1 INDICATIONS AND USAGE

1.1 Primary Immunodeficiency (PI)

HYQVIA is indicated for the treatment of Primary Immunodeficiency (PI) in adults and pediatric patients two years of age and older. This includes, but is not limited to, common variable immunodeficiency (CVID), X-linked agammaglobulinemia, congenital agammaglobulinemia, Wiskott-Aldrich syndrome, and severe combined immunodeficiencies.

1.2 Chronic Inflammatory Demyelinating Polyneuropathy (CIDP)

HYQVIA is indicated for the treatment of chronic inflammatory demyelinating polyneuropathy (CIDP) as maintenance therapy to prevent relapse of neuromuscular disability and impairment in adults.

2 DOSAGE AND ADMINISTRATION

2.1 Recommended Dosage

For subcutaneous use only

The recommended Recombinant Human Hyaluronidase (rHuPH20) dose is 80 U/g Immune Globulin (IgG), which corresponds to 0.5 mL rHuPH20 solution per 10 mL Immune Globulin Infusion (Human), 10% solution for both indications.

The recommended Immune Globulin Infusion (Human), 10% dose is given below.

Primary Immunodeficiency (PI)

Initiation of Treatment with HYQVIA

- For patients previously on another IgG treatment, administer the first dose approximately one week after the last infusion of their previous treatment.
- Gradually increase the dose and frequency from a 1-week dose to a 3-or 4-week dose (see ramp-up schedule in Table 1).
- Initiating treatment at a full monthly dose was not evaluated in the clinical trial.

Table 1: Initial Treatment Interval/Dosage Ramp-Up Schedule
Week | Infusion Number | Dose Interval | Example for 30 grams per 4 weeks
1 | 1st infusion | 1-week-dose | 7.5 grams
2 | 2nd infusion | 2-week-dose | 15 grams
3 | No infusion | Not Applicable (NA) | NA
4 | 3rd infusion | 3-week-dose | 22.5 grams
5 | No infusion | NA | NA
6 | No infusion | NA | NA
7 | 4th infusion (if required) | 4-week-dose | 30 grams

For patients switching from Immune Globulin Intravenous (Human) [IGIV] treatment:

- Administer HYQVIA at the same dose and frequency as the previous intravenous treatment, after the initial dose ramp-up.

For patients at risk for measles exposure:

- If a patient has been exposed to measles, administer a dose of HYQVIA as soon as possible and within 6 days of exposure. A dose of 400 mg/kg should provide a serum level >240 mIU/mL of measles antibodies for at least two weeks.
- If a patient is at risk of future measles exposure and receives a dose of less than 530 mg/kg every 3 to 4 weeks, the dose should be increased to at least 530 mg/kg. This should provide a serum level of 240 mIU/mL of measles antibodies for at least 22 days after infusion.

For patients naïve to Immune Globulin Subcutaneous (Human) [IGSC] treatment or switching from IGSC treatment:

- Administer HYQVIA at 300 to 600 mg/kg at 3 to 4-week intervals, after initial ramp-up.

Individualization of Dose

- If HYQVIA is administered at the same dose and frequency, the serum IgG levels from HYQVIA should be comparable to serum IgG levels from intravenous treatment.

For dose adjustment:

- Calculate the difference between the patient's serum IgG trough level during HYQVIA treatment and the IgG trough level during the previous intravenous treatment.
- Find this difference (in mg/dL) in the columns of Table 2 and the corresponding amount (in mL) by which to increase or decrease the dose based on the patient's body weight and desired change in IgG trough level.

Table 2: Individualization in Volume Administered per Dosing Interval for Intended Change in IgG Trough Level [Derived using a slope of 3.3 kg/dL] (Difference in IgG Trough Levels)
Body Weight | 100 mg/dL | 200 mg/dL | 300 mg/dL | 400 mg/dL
10 kg | 3 mL | 6 mL | 9 mL | 12 mL
20 kg | 6 mL | 12 mL | 18 mL | 24 mL
30 kg | 9 mL | 18 mL | 27 mL | 36 mL
40 kg | 12 mL | 24 mL | 36 mL | 48 mL
50 kg | 15 mL | 30 mL | 45 mL | 61 mL
60 kg | 18 mL | 36 mL | 55 mL | 73 mL
70 kg | 21 mL | 42 mL | 64 mL | 85 mL
80 kg | 24 mL | 48 mL | 73 mL | 97 mL
90 kg | 27 mL | 55 mL | 82 mL | 109 mL
100 kg | 30 mL | 61 mL | 91 mL | 121 mL
110 kg | 33 mL | 67 mL | 100 mL | 133 mL
120 kg | 36 mL | 73 mL | 109 mL | 145 mL
130 kg | 39 mL | 79 mL | 118 mL | 158 mL
140 kg | 42 mL | 85 mL | 127 mL | 170 mL

Example 1: A patient with a body weight of 80 kg has a measured IgG trough level of 800 mg/dL and the reference trough level is 1000 mg/dL. The trough level difference is 200 mg/dL (1000 mg/dL minus 800 mg/dL). The dose of HYQVIA would be increased by 48 mL (4.8 grams) per dosing interval.

Example 2: A patient with a body weight of 60 kg has a measured IgG trough level of 1000 mg/dL and the reference trough level is 900 mg/dL. The trough level difference is -100 mg/dL (900 mg/dL minus 1000 mg/dL). The dose of HYQVIA would be decreased by 18 mL (1.8 grams) per dosing interval.

HYQVIA can be used to administer a full therapeutic dose in one site up to every four weeks. Adjust the frequency and number of infusion sites taking into consideration volume, total infusion time, and tolerability. Adjust the frequency as needed so that the patient receives the same weekly equivalent dose.

Example 3: When adjusting a dose of 30 grams administered every 3 weeks, administer 40 grams of HYQVIA every 4 weeks. If a higher trough level is required relative to intravenous treatment at 3- or 4-week intervals, increase the dose or decrease the dosing interval. Evaluate the use of a second site or infusing at shorter intervals when the volume of HYQVIA is greater than 600 mL.

If a patient misses a dose, administer the missed dose as soon as possible and then resume scheduled treatments as applicable.

If HYQVIA is administered at a different interval than the previous treatment, either intravenously or subcutaneously, then Table 2 should not be used and the dose of HYQVIA should be adjusted, if necessary, based on clinical response.

Chronic Inflammatory Demyelinating Polyneuropathy (CIDP)

General instruction:

- Before initiating therapy with HYQVIA, calculate the weekly equivalent dose to plan for the ramp-up schedule. Dose and dosing frequency can be adjusted based on the individual clinical response.
- A dose ramp-up schedule is recommended by gradually increasing the SC infusion volume until the full dose is reached to ensure the patients’ tolerability.
- Depending on the treating physician's discretion, in patients who tolerate the first two infusions well, subsequent infusions may be administered by gradually increasing doses and decreasing dose intervals, considering the volume and total infusion time.
- Doses less than or equal to 0.4 g/kg may be administered without a ramp-up provided acceptable patient tolerance.

For patients switching from Immune Globulin Intravenous (Human) [IGIV] treatment:

- Patients switching from intravenous administration of immune globulin must be on stable [Variations in the dosing interval of up to ±7 days or monthly equivalent dose amount of up to ±20% between the subject’s IgG infusions are considered a stable dose.] doses of IGIV.
- Before initiating therapy with HYQVIA, calculate the weekly equivalent dose by dividing the last IGIV dose by the IGIV dose interval in weeks.
- The starting dose and dosing frequency of HYQVIA is the same as the patient’s previous IGIV treatment. The typical dosing interval range in the clinical trial for HYQVIA was 4 weeks. For patients with less frequent IGIV dosing (greater than 4 weeks), the dosing interval can be converted to 3 or 4 weeks while maintaining the same monthly equivalent IgG dose.
- Administer the calculated one-week dose (1st infusion) two weeks after the last IGIV infusion as directed in section 2.3. One week after the first HYQVIA dose, administer another weekly equivalent dose (2nd infusion).
- A ramp-up period can take up to 9 weeks (Table 3), depending on the dosing interval and tolerability.

Table 3: IGIV to HYQVIA Infusion Dose Ramp-up Schedule in Study 1
Week [Clock starts one week after the last IGIV dose is administered. Week 1 is the week that starts one week after the last IGIV dose.] | Infusion Number | Dose Interval | Example for 100 g every 4 weeks
1 | No infusion | Not applicable (NA) | NA
2 | 1st infusion | 1-week-dose | 25g
3 | 2nd infusion | 1-week-dose | 25g
4 | 3rd infusion | 2-week-dose | 50g
5 | No infusion | NA | NA
6 | 4th infusion | 3-week-dose | 75g
7 | No infusion | NA | NA
8 | No infusion | NA | NA
9 | 5th infusion | 4-week-dose | 100g (Full dose reached)

2.2 Preparation and Handling

- Visually inspect both vials of HYQVIA for discoloration and particulate matter prior to administration.
  - The appearance of the Immune Globulin Infusion (Human), 10% of HYQVIA can vary from clear or slightly opalescent and colorless or pale yellow.
  - The appearance of the rHuPH20 of HYQVIA should be clear and colorless.
  - Do not use either component of HYQVIA if either solution is cloudy or has particulates.
- Allow refrigerated product to come to room temperature before use. Do not apply heat or place in microwave.
- Do not shake HYQVIA.
- Do not mix the rHuPH20 and the Immune Globulin Infusion (Human), 10% of HYQVIA into the same container prior to administration.
- Do not mix or administer components of HYQVIA with other products. Administer components of HYQVIA sequentially. Do not use either component alone.
- Flush the infusion line with normal saline or Dextrose 5% in water (D5W) if required.
- HYQVIA contains no preservative. Discard any unused product according to local standards for biohazard products.

2.3 Administration

HYQVIA should be administered by a healthcare professional, caregiver or self-administered by the patient after appropriate training.

- Infusion of Immune Globulin Infusion (Human), 10% requires an infusion pump capable of infusing a patient’s therapeutic dose at infusion rates up to 300 mL/hr/site. The pump must have the ability to titrate the flow rate up or down if required to improve tolerability. To ensure maximum flow rates, use a subcutaneous needle set that is 24 gauge and labeled for high flow rates.
- Infusion site leakage can occur during or after subcutaneous administration of immunoglobulin, including HYQVIA. Consider using longer needles (14 or 12 mm rather than 9 mm) and/or more than one infusion site.
- Infuse the two components of HYQVIA sequentially, beginning with the rHuPH20. If using two or three infusion sites, divide the rHuPH20 evenly between all sites.
- Initiate infusion of the full dose of the Immune Globulin Infusion (Human), 10% through the same subcutaneous needle set within approximately 10 minutes of the rHuPH20 infusion. For each full or partial vial of Immune Globulin Infusion (Human), 10% used, administer the entire contents of the rHuPH20 vial.

Selection of Infusion Site(s)

The suggested site(s) for the infusion of HYQVIA are the abdomen and thighs. If two sites are used, the two infusion sites should be on opposite sides of the body. If using three infusion sites, the sites should be at least 10 cm apart. Avoid bony prominences, or areas that are scarred, inflamed, or infected.

Volume per Site

Primary immunodeficiency (PI)

Administer up to 600 mL per site for patients whose body weight is greater than or equal to 40 kg and up to 300 mL per site for patients whose body weight is less than 40 kg.

A second site can be used at the discretion of the physician and patient based on tolerability and total volume. If a second site is used, administer half the total volume of rHuPH20 of HYQVIA in each site.

Chronic Inflammatory Demyelinating Polyradiculoneuropathy (CIDP)

On a given infusion day, the maximum infusion volume should not exceed 1200 mL for patients weighing ≥40 kg or 600 mL for patients weighing <40 kg. If the maximum daily dose limit is exceeded or the patient cannot tolerate the infusion volume, the dose may be administered over multiple days in divided doses with 48 to 72 hours between doses to allow absorption of infusion fluid at the infusion site(s). The dose can be administered at 1, 2, or 3 infusion sites with a maximum infusion volume of 600 mL per site (or as tolerated). If using three sites, the maximum is 400 mL per site.

Rate of Infusion

Primary immunodeficiency (PI)

Administer the rHuPH20 of HYQVIA at an initial rate per site of approximately 1 to 2 mL per minute, or as tolerated.

Administer Immune Globulin Infusion (Human), 10% of HYQVIA at rates as shown in Table 4 for the initial infusions. If the patient tolerates these infusions at the full dose and maximum rate, adjust both the time intervals and number of rate changes of the ramp-up used for successive infusions at the discretion of the physician and patient.

Table 4: Recommended Immune Globulin Infusion (Human), 10% Infusion Rates
 | First 2 Infusions |  | Subsequent 2 or 3 Infusions
 | Patients <40 kg (<88lbs) | Patients ≥40 kg (≥88lbs) | Patients <40 kg (<88lbs) | Patients ≥40 kg (≥88lbs)
Intervals | Rate per site | Rate per site | Rate per site | Rate per site
Minutes | mL per hour | mL per hour | mL per hour | mL per hour
5 - 15 | 5 | 10 | 10 | 10
5 - 15 | 10 | 30 | 20 | 30
5 - 15 | 20 | 60 | 40 | 120
5 - 15 | 40 | 120 | 80 | 240
Remainder of infusion | 80 | 240 | 160 | 300

Chronic Inflammatory Demyelinating Polyradiculoneuropathy (CIDP)

The full dose of rHuPH20 solution is infused at a rate of 1 to 2 mL per minute (60 mL to 120 mL/hr) per infusion site or as tolerated. Immune Globulin Infusion, (Human), 10% can be administered through the same subcutaneous needle set within approximately 10 minutes after the rHuPH20 infusion is completed.

Patients with body weight of 40 kg or above

The Immune Globulin Infusion (Human), 10% should be infused at an initial rate of 10 mL per hour per infusion site. If tolerated, the rate of the administration may be increased at intervals of 5 to 15 minutes and to a maximum infusion rate of 240 mL per hour per infusion site for the initial one or two infusions. For subsequent infusions the rate can be adjusted to a maximum of 300 mL per hour per infusion site.

Patients with body weight under 40 kg

The Immune Globulin Infusion, (Human), 10% should be infused at an initial rate of 5 mL per hour per infusion site. If well tolerated, the rate of the administration may be increased at intervals of 5 to 15 minutes and to a maximum infusion rate of 80 mL per hour per infusion site for the initial one or two infusions. For subsequent infusions the rate can be adjusted to a maximum of 160 mL per hour per infusion site.

Instructions for Administration

To administer HYQVIA using the FDA-cleared Vial Access Devices (VAD), refer to the Instructions For Use (IFU) provided with the VAD. Note: Use the VAD to administer HYQVIA in adult patients only.

To administer HYQVIA using a needle or needle-less transfer device, refer to the following instructions below.

Use aseptic technique when preparing and administering HYQVIA for infusion.

For more detail on steps, see accompanying Information for Patients.

1. Inspect the vials: Inspect for clarity, color, and expiration date(s).

2. Prepare for infusion:

- Gather supplies: HYQVIA dual vial unit(s), ancillary supplies, sharps container and infusion pump (program pump per physician recommendation following manufacturer’s instructions).
- Prepare a clean work area.
- Wash hands.
- If the Immune Globulin Infusion (Human), 10% and rHuPH20 are pooled into separate containers, skip to Step 5.

3. Prepare the rHuPH20 of HYQVIA (Labeled as “HY”):

- Remove the purple protective cap and ensure the blue vial caps are removed.
- Wipe each stopper with a sterile alcohol wipe and allow to dry.
- Attach a syringe to a needle/needle-less transfer device. A sterile needle or needle-less transfer device [(18-22) gauge sterile needle] may be used for all vial sizes. Position the sharp tip of the needle/needle-less transfer device over the center of the vial stopper and insert it at a 90-degree angle. Inject air and then draw the full contents of each vial labeled “HY” into a single syringe, if possible.
- Attach the syringe containing the rHuPH20 to the subcutaneous needle set and prime up to the needle hub.

4. Prepare Immune Globulin Infusion (Human), 10% of HYQVIA (Labeled as “IG”):

- Wipe each stopper with a sterile alcohol wipe and allow to dry.
- Transfer the vial(s) labeled “IG” using one of the following methods:
  - Pool into an infusion bag, using a transfer device per manufacturer’s directions. Attach and prime the pump administrating tubing; or
  - Directly spike the vial using a vented pump administration tubing and prime as directed.

If using a syringe driver, transfer into the syringe(s), preferably using a vented spike.

5. Prepare the infusion site(s):

- Potential sites for infusion include the middle to upper abdomen and thigh.
- Avoid: bony prominences, blood vessels, scars, or areas that are inflamed or infected.
- If two sites are desired, a bifurcated needle set may be used on opposite sides of the body.
- Rotate sites by choosing opposite sides of the body between successive infusions.
- Cleanse the infusion site(s) with a sterile alcohol wipe beginning at the center of each infusion site and moving outward in a circular motion. Allow the infusion site(s) to dry.

6. Insert and secure the 24-gauge subcutaneous needle:

- Pinch at least one inch of skin between two fingers. Insert the needle at a 90-degree angle into the subcutaneous tissue and secure the needle with sterile tape and check the placement.
- If using the push method:
  - Gently pull back on the plunger of the attached syringe and monitor for any blood return in the tubing.
  - If blood is seen in the tubing, remove and discard the needle and repeat steps 3, 5, and 6 with a new subcutaneous needle and infusion site.
- If using the pump method:
  - Close the clamp above the lower port of the pump tubing.
  - Clean the lower port with an alcohol swab and allow to dry, for at least 30 seconds.
  - Attach a 5 mL syringe to the lower port of the pump tubing.
  - Pull back gently on the syringe plunger. If no blood, remove the syringe and open the lower port clamp.
- Secure the needle in place with a sterile protective dressing.

7. Administer the rHuPH20 of HYQVIA:

- If using push method:
  - Infuse the rHuPH20manually at an initial rate of approximately 1 to 2 mL per minute per infusion site and increase as tolerated.
- If using a pump method:
  - start at an initial rate at 60 mL to 120 mL/hr per infusion site and may increase as tolerated up to 300 mL/hr.
- If more than one site is used, divide the contents equally between sites. At the end of infusion, disconnect the empty syringe and attach the pump tubing/syringe containing the Immune Globulin Infusion (Human), 10% of HYQVIA to the same subcutaneous needle set.

8. Administer the Immune Globulin Infusion (Human), 10% of HYQVIA:

Within approximately 10 minutes of completing the infusion of the rHuPH20 of HYQVIA, start the variable rate program of the infusion pump to initiate the infusion of the full therapeutic dose of Immune Globulin Infusion (Human), 10% of HYQVIA. At the end of infusion, flush the infusion tubing up to the needle with normal saline or Dextrose 5% in water (D5W), if required.

9. Remove subcutaneous needle(s) from the infusion site(s):

After the infusion is complete, remove the needle set and cover with a protective dressing. Discard any partially used vial(s) and disposable supplies in accordance with local requirements.

10. Document the infusion:

Remove the peel-off label from each Immune Globulin Infusion (Human), 10% vial of HYQVIA used and affix to the patient’s treatment record or infusion log. In addition, record the time, date, dose, infusion site location and any reactions after each infusion.

For self-administration, provide the patient with instructions and training for infusion in the home or other appropriate setting.

3 DOSAGE FORMS AND STRENGTHS

HYQVIA is a dual vial unit consisting of one vial of a liquid solution containing Immune Globulin Infusion (Human), 10% and one vial of a liquid solution containing 160 U/mL rHuPH20.

HYQVIA is available in the following strengths:

Table 5: HYQVIA strengths
Immune Globulin Infusion (Human), 10% |  | rHuPH20
Volume | Grams Protein | Volume | Units
25 mL | 2.5 | 1.25 mL | 200
50 mL | 5.0 | 2.5 mL | 400
100 mL | 10.0 | 5.0 mL | 800
200 mL | 20.0 | 10.0 mL | 1600
300 mL | 30.0 | 15.0 mL | 2400

4 CONTRAINDICATIONS

HYQVIA is contraindicated in:

- Patients who have had a history of anaphylactic or severe systemic reactions to the administration of IgG.
- IgA deficient patients with antibodies to IgA and a history of hypersensitivity.
- Patients with known systemic hypersensitivity to hyaluronidase including rHuPH20 of HYQVIA.
- Patients with known systemic hypersensitivity to human albumin (in the hyaluronidase solution)].

5 WARNINGS AND PRECAUTIONS

5.1 Hypersensitivity Reactions

Severe hypersensitivity reactions may occur after treatment with immune globulin products, including HYQVIA, even in patients previously treated with immune globulin products. In case of hypersensitivity, discontinue the HYQVIA infusion immediately and institute appropriate treatment.

Immune Globulin Infusion (Human), 10% of HYQVIA contains IgA (average concentration of 37µg/mL). Patients with antibodies to IgA potentially are at greater risk of developing potentially severe hypersensitivity and anaphylactic reactions.

5.2 Thrombosis

Thrombosis has been reported to occur following treatment with immune globulin products, including HYQVIA. Risk factors may include advanced age, prolonged immobilization, hypercoagulable conditions, history of venous or arterial thrombosis, use of estrogens, indwelling central vascular catheters, hyperviscosity, and cardiovascular risk factors. Thrombosis may occur in the absence of known risk factors.

Ensure adequate hydration in patients before administration of HYQVIA. For patients at risk of thrombosis, administer HYQVIA at the minimum dose and infusion rate practicable. Monitor patients for signs and symptoms of thrombosis.

Consider baseline assessment of blood viscosity in patients at risk for hyperviscosity, such as those with cryoglobulins, fasting chylomicronemia/markedly high triacylglycerols (triglycerides), or monoclonal gammopathies. [see Boxed Warning, Dosage and Administration (2)].

5.3 Immunogenicity of rHuPH20

Eighteen percent (15 of 83) of patients receiving HYQVIA in PID clinical studies developed non-neutralizing antibodies to the rHuPH20 component. The potential exists for such antibodies to cross-react with endogenous Hyaluronidase (PH20), which is known to be expressed in the adult male testes, epididymis, and sperm. It is unknown whether these antibodies can interfere with fertilization in humans. The clinical significance of these antibodies is not known.

Clinical studies in CIDP based on 3,188 rHuPH20 infusions in 132 patients revealed one incidence of anti-rHuPH20 neutralizing antibody positivity. Elevation in neutralizing antibody titers was transient and occurred at a single measurement over a 3-year follow-up period. No efficacy or safety issues were identified with the occurrence of neutralizing antibody positivity.

5.4 Aseptic Meningitis Syndrome

Aseptic meningitis syndrome (AMS) may occur with immune globulin products, including HYQVIA. Signs and symptoms of AMS include severe headache, nuchal rigidity, drowsiness, fever, photophobia, painful eye movements, nausea and vomiting. AMS usually begins within several hours to 2 days following immune globulin treatment. Conduct neurological examination on patients exhibiting symptoms and signs of AMS, including Cerebrospinal fluid (CSF) studies, to rule out other causes of meningitis. CSF studies frequently reveal pleocytosis up to several thousand cells per cubic millimeter, elevated protein levels up to several hundred mg/dL, and negative culture results. Discontinuation of IgG treatment has resulted in remission of AMS within several days without sequelae.

5.5 Hemolysis

Hemolysis may occur with immune globulin products, including HYQVIA due to the presence of blood group antibodies that may act as hemolysins and induce in vivo coating of red blood cells (RBC). This may cause a positive direct antiglobulin test [DAT (Coombs test)]. Delayed hemolytic anemia can develop after HYQVIA therapy due to enhanced RBC sequestration [see Adverse Reactions (6)].

Monitor patients for signs and symptoms of hemolysis. If signs and symptoms of hemolysis are observed, perform additional confirmatory laboratory testing.

5.6 Renal Injury

Renal injury including acute renal failure, acute tubular necrosis, proximal tubular nephropathy, and osmotic nephrosis may occur after treatment with immune globulin products, including HYQVIA.

Ensure patients are not volume depleted before administering HYQVIA. In patients who are at risk of renal injury because of pre-existing renal insufficiency or predisposition to acute renal failure (such as diabetes mellitus, age greater than 65, volume depletion, sepsis, paraproteinemia, or patients receiving known nephrotoxic drugs, etc.), administer HYQVIA at the minimum rate of infusion practicable [see Dosage and Administration (2.3)].

Assess renal function, including measurement of blood urea nitrogen (BUN), serum creatinine, and urine output in patients receiving HYQVIA prior to initial infusion and at appropriate intervals thereafter. If renal function deteriorates, consider discontinuation of HYQVIA [see Dosage and Administration (2.3)].

5.7 Spread of Localized Infection

Infusion into or around an infected area can spread a localized infection. Do not infuse HYQVIA into these areas due to potential risk of spreading a localized infection.

5.8 Transfusion-Related Acute Lung Injury

Transfusion-Related Acute Lung Injury (TRALI) may occur with intravenously administered immune globulin products symptoms typically occur within 1 to 6 hours after treatment and may include severe respiratory distress, pulmonary edema, hypoxemia, normal left ventricular function, and fever.

Monitor patients for signs and symptoms of TRALI. If TRALI is suspected, conduct an evaluation, including appropriate tests for the presence of anti-neutrophil and anti-HLA antibodies in both the product and patient serum. Manage patients using oxygen therapy with ventilatory support as appropriate.

5.9 Transmissible Infectious Agents

There is risk of transmission of infectious disease or agents including viruses, the variant Creutzfeldt-Jakob disease (vCJD) agent, and the Creutzfeldt-Jakob disease agent with HYQVIA administration because it is manufactured using human blood. The risk of infectious agent transmission is minimized by plasma donor screening, donation testing, and manufacturing steps proven to inactivate and remove bloodborne pathogens.

Report all infections thought to be possibly transmitted by HYQVIA to Takeda Pharmaceuticals U.S.A., Inc. at 1-877-TAKEDA-7 (1-877-825-3327) (In the U.S.).

5.10 Interference with Laboratory Tests

- After infusion of IgG, the transitory rise of the various passively transferred antibodies in the patient’s blood may yield false positive serological testing results, with the potential for misleading interpretation. Passive transmission of antibodies to erythrocyte antigens (e.g., A, B, and D) may cause a positive direct or indirect antiglobulin (Coombs’) test.
- Infusions of immune globulin products can lead to false positive readings in assays that depend on detection of ß-D-glucans for diagnosis of fungal infections; this may persist during the weeks following infusion of the product.

6 ADVERSE REACTIONS

6.1 Clinical Trials Experience

Because clinical studies are conducted under widely varying conditions, adverse reaction rates observed in clinical studies of a product cannot be directly compared to rates in the clinical studies of another product and may not reflect the rates observed in clinical practice.

Primary Immunodeficiency (PI)

Immune Globulin Infusion (Human), 10% administered intravenously: Prior to initiation of treatment with HYQVIA, 87 patients received 365 infusions of Immune Globulin Infusion (Human), 10% encompassing 22.2 patient-years. Among the 87 patients treated, 56 (64.4%) experienced 1 or more adverse reactions. Among the 365 intravenous infusions, 158 adverse reactions occurred for a rate per infusion of 0.43.

A total of 1,359 infusions of HYQVIA were administered during the trial; 230 of these infusions occurred during the ramp-up period and the other 1,129 occurred during the observation period. During the observation period, 81 patients received 1,129 infusions of HYQVIA; of those, 67 (82.7%) experienced one or more adverse reactions. Among the 1,129 HYQVIA infusions, 456 adverse reactions occurred for a rate per infusion of 0.40. Seven of these adverse reactions were severe, defined as marked impairment of function, can lead to temporary inability to resume normal life pattern, requires prolonged intervention and/or results in sequelae.

Adverse reactions occurring in greater than 5% of patients associated with infusions of HYQVIA vs. Immune Globulin Infusion (Human), 10% given intravenously are shown in Table 6. The majority of these adverse reactions was mild to moderate in severity and did not necessitate discontinuing the infusions. Mild is defined as transient discomfort that resolves spontaneously or with minimal intervention; moderate is defined as limited impairment of function that resolves spontaneously or with minimal intervention with no sequelae. No serious adverse reactions occurred during the HYQVIA clinical trials.

Table 6: Adverse Reactions [Causally related adverse events and/or temporally associated adverse events occurring within 72 hours.] in greater than 5% of Patients Associated with Infusions of HYQVIA vs. Immune Globulin Infusion (Human), 10% (IGIV) Given Intravenously
 | HYQVIA |  | IGIV Given Intravenously
Adverse Reactions [Excluding infections] | Number of Patients (%) N= 81 | Number of Adverse Reactions per Infusion (Rate [Rate= total number of events divided by total number of infusions.]) N = 1129 | Number of Patients (%) N=87 | Number of Adverse Reactions per Infusion (Rate) N = 365
Local ARs | 42 (51.9%) | 234 (0.21) | 4 (4.6%) | 4 (0.01)
Systemic ARs | 55 (67.9%) | 222 (0.20) | 54 (62.1%) | 154 (0.42)
Headache | 17 (21%) | 40 (0.04) | 22 (25.3%) | 42 (0.12)
Fatigue | 9 (11.1%) | 16 (0.01) | 8 (9.2%) | 10 (0.03)
Nausea | 6 (7.4%) | 12 (0.01) | 10 (11.5%) | 10 (0.03)
Pyrexia | 6 (7.4%) | 11 (0.01) | 6 (6.9%) | 7 (0.02)
Vomiting | 6 (7.4%) | 11 (0.01) | 5 (5.7%) | 7 (0.02)

Six patients, 2 children and 4 adults, withdrew from the trial during the efficacy treatment period with HYQVIA due to mild to moderate adverse reactions. One child withdrew due to local pain and one due to fever, vomiting, and headaches. Of the four adults, two withdrew due to local pain and swelling, one had moderate swelling that transiently extended from the abdominal infusion site to the genitalia, and one had back injury.

Antibodies binding to rHuPH20: A total of 15 out of 83 patients in the clinical trial who were treated with HYQVIA developed an antibody capable of binding to rHuPH20. These antibodies were not capable of neutralizing rHuPH20.

In the clinical trial, no temporal association between adverse reactions and the presence of antibodies capable of binding to the Recombinant Human Hyaluronidase of HYQVIA could be demonstrated. There was no increase in the incidence or severity of adverse reactions in patients who developed antibodies to rHuPH20 of HYQVIA. In all patients, antibody titers decreased despite continued treatment.

The effect of exposure to antibodies capable of binding to rHuPH20 of HYQVIA for periods longer than this clinical trial has not been evaluated.

The local adverse reactions are listed by frequency in Table 7. Mild swelling around the infusion site was present in most infusions due to the large volumes infused, but in general was not considered to be an adverse reaction unless it caused discomfort. Among the 234 local adverse reactions, three were severe (infusion site pain, infusion site swelling and infusion site edema that extended from the abdominal infusion site to the genitalia); all were transient and resolved without sequelae. More than 98% of local reactions were either mild (70.5%) or moderate (28.2%) in severity.

Table 7: Most Frequent Local Adverse Reactions Reported in greater than 1% of Infusion During Treatment With HYQVIA
Infusion Site Reaction | Number and Rate of Reactions per Infusion (N=1129)
Discomfort/pain | 122 (0.11)
Erythema | 32 (0.03)
Swelling/Edema | 35 (0.03)
Pruritus | 22 (0.02)
Rate per infusion = total number of events divided by total number of infusions.

During the combined efficacy and extension trials encompassing more than 3 years, the local adverse reaction rate was 2.6 per patient-year. During the first 12-month period (months 1- 12), the rate was 3.68 local adverse reactions per patient-year. During the subsequent 12-month period (months 13-24), the rate declined to 2.12 local adverse reactions per-patient year. Finally, during the third 12-month period (months 25-36), the rate further declined to 0.37 local adverse reactions per patient-year.

Sixty-six of the 68 patients who completed the efficacy clinical trial enrolled in a prospective, open-label, multicenter extension trial to assess the long-term safety and tolerability of HYQVIA. Sixty-three of 66 patients enrolled received HYQVIA and 3 received IGIV. Of the 63 patients who received HYQVIA, 48 completed the extension trial. The cumulative exposure of HYQVIA across the two trials was 188 subject-years and 2,959 infusions, and a maximum exposure of 188 weeks or up to approximately 3.5 years. There were no clinically observable changes in the skin or subcutaneous tissue in either the efficacy or extension clinical trials.

Pediatric population in PI:

HYQVIA was evaluated in a pivotal efficacy and safety study in 44 pediatric patients (aged 2 to 16 years of age). Results from the interim data analysis, where all patients completed 12 months of participation (one year of observation period) in the study, indicated similar safety profiles to adults [see Clinical Pharmacology (12.3), and Clinical Studies (14.1)].

Chronic Inflammatory Demyelinating Polyneuropathy (CIDP)

The safety of HYQVIA in adult patients with CIDP was evaluated in 100 unique patients in a randomized, placebo-controlled study (Study 1) and a single-arm, open-label, extension study (Study 2). A total of 3188 infusions of HYQVIA were administered during these 2 studies [see Clinical Studies (14.2)].

Development of antibodies to rHuPH20: A total of 15 patients (15%) who were treated with HYQVIA in Studies 1 and 2 developed high-binding anti-rHuPH20 antibody titers (≥1:160). A total of 7 patients (11.3%) who were treated with HYQVIA in Study 1 and a total of 14 patients (17.7%) in Study 2 developed high-binding anti-rHuPH20 antibodies (≥1:160). Of the 7 patients in Study 1, 6 continued to have high-binding antibodies in Study 2, and 1 subject did not enter Study 2. Eight of the 14 patients developed high-binding antibodies during Study 2. The occurrence of high-binding antibodies was not associated with an increased rate of TEAEs. One subject had a transient positivity of neutralizing antibodies which were not associated with any TEAE consistent with decreased rHuPH20 effect (in Study 2). The binding antibody positivity rate was comparable to the rates reported in other development programs.

Study 1

A total of 62 patients received HYQVIA and a total of 598 infusions of HYQVIA were administered. Adverse reactions (ARs) occurring in >5% of patients with CIDP treated with HYQVIA in Study 1 are shown in Table 8.

Table 8: Adverse Reactions [Causally related adverse events and/or temporally associated adverse events occurring within 72 hours.] in >5% of Patients with CIDP Treated with HYQVIA (Study 1: All Safety Patients)
ARs [Excluding infections] | HYQVIA Number of Patients (%) N = 62 | HYQVIA Number of ARs per Infusion (Rate [Rate=total number of events divided by total number of infusions.]) N = 598 | Placebo Number of Patients (%) N=70 | Placebo Number of ARs per Infusion (Rate) N=644
• Local ARs | 17 (27.4) | 103 (0.17) | 5 (7.1) | 13 (0.02)
• Systemic ARs | 18 (29.0) | 44 (0.07) | 7 (10.0) | 14 (0.02)
- Nausea | 7 (11.3) | 8 (0.01) | 0 | 0
- Fatigue | 5 (8.1) | 7 (0.01) | 1 (1.4) | 1 (<0.01)
- Pruritus | 5 (8.1) | 14 (0.02) | 1 (1.4) | 1 (<0.01)
- Headache | 4 (6.5) | 9 (0.02) | 5 (7.1) | 12 (0.02)
- Pyrexia | 4 (6.5) | 6 (0.01) | 0 | 0
AR=adverse reactions

Blood pressure elevation was reported in 4 patients (6.5%) treated with HYQVIA in this study, including 2 patients with a history of hypertension on antihypertensive medications. Three of the 4 patients had events which were causally related and/or temporally associated (occurring within 72 hours).

A total of 4 patients (3.0%) experienced adverse events (AEs) that led to discontinuation from the study; Three (3) patients in the HYQVIA group and 1 in the placebo group. The AEs leading to discontinuation in the 3 HYQVIA patients included: a cerebrovascular accident in 1 subject (who had coexisting cardiovascular risk factors), infusion site edema and infusion site pain in another subject, and nausea and chills in the third subject.

The most frequent local ARs in Study 1 are listed by frequency in Table 9. All HYQVIA local reactions (100%) were either mild (88.41%) or moderate (11.59%) in severity.

Table 9: Most Frequent Local Adverse Reactions Reported in >1% of Infusion with CIDP Treated with HYQVIA (Study 1: All Safety Patients)
Infusion Site Reaction | HYQVIA Number of ARs per Infusion (%) N = 598 | Placebo Number of ARs per Infusion (%) N = 644
Discomfort/pain | 39 (6.5%) | 12 (1.9%)
Swelling/edema | 38 (6.4%) | 6 (0.9%)
Erythema | 36 (6.0%) | 0
Pruritus | 15 (2.5%) | 0
AR=adverse reaction

Study 2

At the time of the interim analysis, 79 patients received HYQVIA and a total of 2,590 infusions of HYQVIA were administered. Adverse reactions occurring in >5% of patients with CIDP treated with HYQVIA in Study 2 are shown in Table 10.

Table 10: Adverse Reactions [Causally related adverse events and/or temporally associated adverse events occurring within 72 hours.] in >5% of Patients with CIDP Treated with HYQVIA (Study 2: All Safety Patients)
ARs [Excluding infections] | Number of Patients (%) N = 79 | Number of ARs per Infusion (Rate [Rate=total number of events divided by total number of infusions.]) N = 2,590
• Local ARs | 19 (24.1) | 251 (0.10)
• Systemic ARs | 32 (40.5) | 249 (0.10)
- Headache | 16 (20.3) | 71 (0.03)
- Pyrexia | 12 (15.2) | 58 (0.02)
- Nausea | 7 (8.9) | 9 (<0.01)
- Erythema | 6 (7.6) | 75 (0.03)
- Fatigue | 6 (7.6) | 9 (<0.01)
- Abdominal pain | 5 (6.3) | 8 (<0.01)
- Back pain | 4 (5.1) | 4 (<0.01)
- Lipase increased | 4 (5.1) | 4 (<0.01)
- Pain in extremity | 4 (5.1) | 11 (<0.01)
AR=adverse reactions

Blood pressure elevation was reported in 5 patients (6.3%) in this study, including 1 subject with a history of hypertension on antihypertensive medications. One (1) of the 5 patients had an event which was causally related and/or temporally associated (occurring within 72 hours).

A total of 3 patients (3.8%) experienced AEs that led to discontinuation from the study and 1 subject (1.3%) died prior to the time of the interim analysis. The AEs leading to discontinuation in the 3 patients included mantle cell lymphoma in 1 subject, muscular weakness and worsening of CIDP in another subject, and abdominal pain in the third subject. The cause of death in the 1 subject was cholangiocarcinoma.

The most frequent local ARs in Study 161505 are listed by frequency in Table 11. Most of the local reactions (95%) were either mild (85.44%) or moderate (9.34%) in severity.

Table 11: Most Frequent Local Adverse Reactions Reported in >1% of Infusion with CIDP Treated with HYQVIA (Study 2: All Safety Patients)
Infusion Site Reaction | Number of ARs per Infusion (%) N = 2,590
Erythema | 225 (8.7%)
Swelling/edema | 58 (2.2%)
AR=adverse reaction

6.2 Postmarketing Experience

Because postmarketing reporting of adverse reactions is voluntary and from a population of uncertain size, it is not always possible to reliably estimate the frequency of these reactions or establish a causal relationship to product exposure.

In addition to the adverse reactions listed above in clinical trials, the following adverse reactions have been reported in the postmarketing experience:

Immune System Disorder: Hypersensitivity

General Disorder and Administration Site Conditions: Influenza-like illness, Infusion site leaking

Postmarketing Experience of Immune Globulin Products

The following adverse reactions have been identified and reported during the postmarketing use of Immune Globulin products administered subcutaneously:

Anaphylactic reaction, Tremor, Tachycardia, Hypotension, Infusion related reaction, Dyspnea, Paresthesia oral, Dermatitis allergic, Injection site rash, and Alanine aminotransferase increased.

7 DRUG INTERACTIONS

Passive transfer of antibodies can transiently impair the immune responses to live attenuated virus vaccines, such as mumps, rubella, and varicella for up to 6 months and for a year or more to measles.

Admixtures of HYQVIA with other drugs solutions have not been evaluated. Do not mix or administer components of HYQVIA with other products.

8 USE IN SPECIFIC POPULATIONS

8.1 Pregnancy

Risk Summary

Limited human data are available to assess the presence or absence of drug-associated risk in pregnancy. In a postmarketing pregnancy study, two out of 5 infants born to mothers taking HYQVIA during pregnancy had congenital abnormalities (1 cleft lip and 1 talipes calcaneovalgus). Animal reproduction studies have not been conducted with the Immune Globulin Infusion (Human), 10% component of HYQVIA. Immune globulins increasingly cross the placenta from maternal circulation after 30 weeks of gestation. There was no evidence of teratogenicity in animal studies for rHuPH20, (a component of HYQVIA). The effects of antibodies to the rHuPH20 on the human embryo or fetal development are unknown. It is not known whether HYQVIA can cause fetal harm when administered to a pregnant woman or if it can affect reproductive capacity. HYQVIA should be given to a pregnant woman only if clearly needed.

The estimated background risk of major birth defects and miscarriage for the indicated population is unknown. All pregnancies have a background risk of birth defect, loss, or other adverse outcomes. In the U.S. general population, the background risk of major birth defects and miscarriage in clinically recognized pregnancies is 2% to 4% and 15% to 20%, respectively.

Data

Human data:

Nine women treated with HYQVIA were enrolled in a prospective, uncontrolled, open-label, multicenter post-authorization Pregnancy Registry. Seven mothers continued HYQVIA, and two mothers were treated with immune globulin other than HYQVIA during the pregnancy. One mother discontinued from the registry before the expected delivery. Of the eight pregnancies with known outcomes, there were eight live births. There were no specified labor or delivery complications. Two out of 5 infants whose mothers took HYQVIA during pregnancy had congenital abnormalities (cleft lip without cleft palate and talipes calcaneovalgus). Data from the HYQVIA Pregnancy Registry are insufficient to establish causality. The interpretation of the registry findings is limited by the small sample size, by the potential that selection bias may have increased enrollment of mothers of infants with congenital abnormalities, the absence of fetal outcomes in some exposed maternal-fetal pairs, and incomplete data on other potential etiologies.

The following adverse events were identified in post-approval reports: spontaneous abortions and fetal deaths. The following congenital anomalies were identified in post-approval reports in infants whose mothers took HYQVIA during pregnancy: cleft palate, atrial septal defect, ventricular septal defect, cleft lip, hypoplastic left heart syndrome (aortic atresia, mitral valve atresia), endocardial fibroelastosis, and tricuspid valve incompetence. Because these events are reported voluntarily from a population of uncertain size, it is not always possible to reliably estimate their frequency or establish a causal relationship to drug exposure.

Animal data:

Animal reproduction studies have not been conducted with Immune Globulin Infusion (Human), 10% component of HYQVIA.

Development and reproductive toxicology studies have been conducted with rHuPH20 in mice and rabbits [see Nonclinical Toxicology (13.2)]. No adverse effects on pregnancy were associated with anti-rHuPH20 antibodies at a dose of 3 mg/kg rHuPH20 in mice, which is 4,800 times higher than the typical monthly human dose. No teratogenicity or signs of maternal toxicity were observed at doses up to 18 mg/kg, which is 28,800 times higher than the typical monthly human dose. Doses of 9 and 18 mg/kg (14,400 and 28,800 times higher than the typical monthly human dose) in mice were associated with reduced fetal weight and an increased number of fetal resorptions. In these studies, maternal antibodies to rHuPH20 were transferred to offspring in utero. The effects of antibodies to the rHuPH20 component of HYQVIA on the human embryo or on human fetal development are unknown.

8.2 Lactation

Risk Summary

It is not known whether HYQVIA can cause harm to the breastfed infant when administered to a lactating woman. The developmental and health benefits of breastfeeding should be considered along with the mother's clinical need for HYQVIA and any potential adverse effects on the breastfed infant from HYQVIA or from the underlying maternal condition. Data from the HYQVIA Pregnancy Registry are insufficient to predict effects on the breastfed child from exposure to HYQVIA through human milk.

Data

Animal data:

In animal studies, maternal antibodies binding to rHuPH20 were transferred to offspring during lactation. No adverse effects on pregnancy or offspring development were associated with anti-rHuPH20 antibodies. The effects of antibodies that bind to rHuPH20 of HYQVIA transferred during human lactation are unknown.

8.3 Females and Males of Reproductive Potential

Risk Summary

Animal studies do not indicate direct or indirect harmful effects of (rHuPH20) with respect to reproductive potential at the doses used for facilitating administration of IG 10% [see Nonclinical Toxicology (13.1)].

8.4 Pediatric Use

Primary Immunodeficiency (PI)

The safety and effectiveness of HYQVIA for the treatment of Primary Immunodeficiency have been established in pediatric patients 2 years and older.

Use of HYQVIA for this indication is supported by evidence from the pivotal efficacy and safety study in 44 pediatric patients (aged 2 to 16 years of age). Results from pre-specified interim data analysis, where all patients completed 12 months of participation (one year of observation period) in the study, indicated similar safety profiles to adults. No pediatric-specific dose requirements were necessary to achieve the desired serum IgG levels. [see Adverse Reactions (6.1), Clinical Pharmacology (12.3), and Clinical Studies (14.1)].

Safety and effectiveness of HYQVIA has not been evaluated in patients <2 years of age.

Chronic Inflammatory Demyelinating Polyneuropathy (CIDP)

The safety and effectiveness of HYQVIA for the treatment of CIDP have not been established in pediatric patients.

8.5 Geriatric Use

Primary Immunodeficiency (PI)

HYQVIA was evaluated in 7 patients over age 65 in the PI clinical trial. The available data are too limited to draw safety conclusions.

Chronic Inflammatory Demyelinating Polyneuropathy

HYQVIA was evaluated in 13 patients over age 65 in the pivotal clinical trial. No clinically significant differences in safety were observed between those 13 elderly patients and the patients 18 to 65 years of age.

Use caution when administering HYQVIA to patients age 65 and over who are judged to be at increased risk of developing thrombosis and acute renal insufficiency [see Boxed Warning, Warnings and Precautions (5.2, 5.6)]. Do not exceed recommended doses and administer HYQVIA at the minimum dose and infusion rate practicable.

11 DESCRIPTION

HYQVIA is a dual vial unit with one vial of Immune Globulin Infusion (Human), 10% and one vial of rHuPH20.

The Immune Globulin Infusion (Human), 10% of HYQVIA is a ready-for-use, sterile, liquid preparation of highly purified and concentrated IgG antibodies. The distribution of the IgG subclasses is similar to that of normal plasma. The Fc and Fab functions are maintained in the primary component. Pre-kallikrein activator activity is not detectable. The Immune Globulin Infusion (Human), 10% of HYQVIA contains 100 mg/mL protein. At least 98% of the protein is IgG, average immunoglobulin A (IgA) concentration is 37µg/mL, and immunoglobulin M (IgM) is present in trace amounts. The Immune Globulin Infusion (Human), 10% of HYQVIA contains a broad spectrum of IgG antibodies against bacterial and viral agents. Glycine (0.25M) serves as a stabilizing and buffering agent. There is no added sugar, sodium, or preservatives. The pH is 4.6 to 5.1. The osmolality is 240 to 300 mOsmol/kg.

The Immune Globulin Infusion (Human), 10% of HYQVIA is manufactured from large pools of human plasma. IgG preparations are purified from plasma pools using a modified Cohn-Oncley cold ethanol fractionation process, as well as cation and anion exchange chromatography.

Screening against potentially infectious agents begins with the donor selection process and continues throughout plasma collection and plasma preparation. Each individual plasma donation used in the manufacture of the Immune Globulin Infusion (Human), 10% of HYQVIA is collected only at FDA approved blood establishments and is tested by FDA licensed serological tests for Hepatitis B Surface Antigen (HBsAg), and for antibodies to Human Immunodeficiency Virus (HIV-1/HIV-2) and Hepatitis C Virus (HCV) in accordance with U.S. regulatory requirements. As an additional safety measure, mini-pools of the plasma are tested for the presence of HIV-1 and HCV by FDA licensed Nucleic Acid Testing (NAT).

To further improve the margin of safety, three dedicated, independent and effective virus inactivation/removal steps have been integrated into the manufacturing and formulation processes, namely solvent/detergent (S/D) treatment, 35 nm nanofiltration, and a low pH incubation at elevated temperature. The S/D process includes treatment with an organic mixture of tri-n-butyl phosphate, octoxynol 9 and polysorbate 80 at 18°C to 25°C for a minimum of 60 minutes.

In vitro virus spiking studies have been used to validate the capability of the manufacturing process to inactivate and remove viruses. To establish the minimum applicable virus clearance capacity of the manufacturing process, these virus clearance studies were performed under extreme conditions (e.g., at minimum S/D concentrations, incubation time and temperature for the S/D treatment). Virus clearance studies for the Immune Globulin Infusion (Human), 10% of HYQVIA performed in accordance with good laboratory practices (Table 12) have demonstrated that:

- S/D treatment inactivates the lipid-enveloped viruses investigated to below detection limits within minutes.
- 35 nm nanofiltration removes lipid-enveloped viruses to below detection limits and reduces the nonlipid enveloped viruses HAV and B19V. As determined by a polymerase chain reaction assay, nanofiltration reduced B19V by a mean log10 reduction factor of 4.8 genome equivalents.
- Treatment with low pH at elevated temperature of 30°C to 32°C inactivates lipid-enveloped viruses and encephalomyocarditis virus (EMCV, model for HAV) to below detection limits, and reduces mice minute virus (MMV, model for B19V).

Table 12: Three Dedicated Independent Virus Inactivation/Removal Steps Mean Log10 Reduction Factors [For the calculation of these RF data from virus clearance study reports, applicable manufacturing conditions were used. Log10 RFs on the order of 4 or more are considered effective for virus clearance in accordance with the Committee for Medicinal Products for Human Use (CHMP, formerly CPMP) guidelines.] (RFs) For Each Virus and Manufacturing Step
Virus type | Enveloped RNA |  |  | Enveloped DNA | Non-enveloped RNA |  | Non-enveloped DNA
Family | Retroviridae | Flaviviridae |  | Herpesviridae | Picornaviridae |  | Parvoviridae
Virus | HIV-1 | BVDV | WNV | PRV | HAV | EMCV | MMV
SD treatment | >4.5 | >6.2 | n.a. | >4.8 | n.d. | n.d. | n.d.
35 nm nanofiltration | >4.5 | >5.1 | >6.2 | >5.6 | 5.7 | 1.4 | 2.0
Low pH treatment | >5.8 | >5.5 | >6.0 | >6.5 | n.d. [No RF obtained due to immediate neutralization of HAV by the anti-HAV antibodies present in the product.] | >6.3 | 3.1
Overall log reduction factor (ORF) | >14.8 | >16.8 | >12.2 | >16.9 | 5.7 | >7.7 | 5.1
Abbreviations: HIV-1, Human Immunodeficiency Virus Type 1; BVDV, Bovine Viral Diarrhea Virus (model for Hepatitis C Virus and other lipid enveloped RNA viruses); WNV, West Nile Virus; PRV, Pseudorabies Virus (model for lipid enveloped DNA viruses, including Hepatitis B Virus); EMCV, Encephalomyocarditis Virus (model for non-lipid enveloped RNA viruses, including Hepatitis A virus [HAV]); MMV, Mice Minute Virus (model for non-lipid enveloped DNA viruses, including B19 virus [B19V]); n.d. (not done), n.a. (not applicable).

The rHuPH20 of HYQVIA is produced from genetically engineered Chinese Hamster Ovary (CHO) cells containing a DNA plasmid encoding for a soluble fragment of human hyaluronidase PH20. The purified hyaluronidase glycoprotein contains 447 amino acids with an approximate molecular weight of 61,000 Daltons [see Clinical Pharmacology (12.1)]. This component is supplied as a sterile, clear, colorless, ready-for-use solution and has an approximate pH of 7.4 and an osmolality of 290 to 350 mOsm. Each vial contains 160 U/mL of rHuPH20 with 8.5 mg/mL sodium chloride, 1.78 mg/mL sodium phosphate dibasic dihydrate, 1.0 mg/mL human albumin, 1.0 mg/mL edentate disodium dihydrate, 0.40 mg/mL calcium chloride dihydrate, and 0.17 mg/mL sodium hydroxide added for pH adjustment. It does not contain preservatives.

Due to comprehensive virus testing at the Master Cell Bank, Working Cell Bank and bulk harvest stage, effective virus reduction during the purification process and use of pharmaceutical grade human albumin as an excipient with no other materials of human or animal origin involved in the manufacturing process, rHuPH20 provides for high margins of safety with respect to viruses.

12 CLINICAL PHARMACOLOGY

12.1 Mechanism of Action

The Immune Globulin Infusion (Human), 10% provides the therapeutic effect of HYQVIA. The Recombinant Human Hyaluronidase of HYQVIA increases dispersion and absorption of the Immune Globulin Infusion (Human), 10%. The Immune Globulin Infusion (Human), 10% of HYQVIA supplies a broad spectrum of opsonizing and neutralizing IgG antibodies against a wide variety of bacterial and viral agents. The Immune Globulin Infusion (Human), 10% also contains a spectrum of antibodies capable of interacting with and altering the activity of cells of the immune system as well as antibodies capable of reacting with cells such as erythrocytes. The role of these antibodies and the mechanisms of action of IgG in the Immune Globulin Infusion (Human), 10% of HYQVIA have not been fully elucidated.

The mechanism of action of immunoglobulins in the treatment of CIDP in adults has not been fully elucidated but may include immunomodulatory effects.

Hyaluronan is a polysaccharide found in the extracellular matrix of connective tissue. It is depolymerized by the naturally occurring enzyme hyaluronidase. Unlike the stable structural components of the interstitial matrix, hyaluronan has a very fast turnover with a half-life of approximately 0.5 days. The rHuPH20 of HYQVIA increases permeability of the subcutaneous tissue by temporarily depolymerizing hyaluronan. In the doses administered, rHuPH20 of HYQVIA acts locally. The effects of the hyaluronidase are reversible, and permeability of the subcutaneous tissue is restored within 24 to 48 hours.

12.3 Pharmacokinetics

Primary Immunodeficiency (PI)

The pharmacokinetics (PK) of HYQVIA was evaluated during a clinical trial of adults with PI after they achieved steady state at their 3- or 4-week dosing interval and underwent individual dose adjustment [see Clinical Studies (14)]. For adults, dose adjustment was based on a comparison of the ratios of the area under the IgG concentration versus time curve (AUC) during intravenous treatment versus during HYQVIA treatment.

The AUC of HYQVIA compared to conventional IGSC administration was 20% higher. The bioavailability of HYQVIA based on weekly AUC was 93.3% relative to IGIV.

The pharmacokinetic parameters of HYQVIA compared with intravenously administered Immune Globulin Infusion (Human), 10% are shown in Table 13. The mean IgG dose in weekly equivalents was 147 mg/kg ± 50 (range 134 to 160 mg/kg). The serum IgG trough levels are comparable: the mean serum IgG trough with HYQVIA was 1077 mg/dL compared with 1095 mg/dL with intravenously administered Immune Globulin Infusion (Human), 10%. Cmax was lower with HYQVIA (1607 mg/dL) than with intravenously administered Immune Globulin Infusion (Human), 10% (2248 mg/dL). Time to reach maximum concentration of IgG following HYQVIA administration was 5 (3.3-5.1) days.

In the extension trial, reducing the dosing interval from 4 to 2 weeks resulted in a mean increase of 13% in serum IG trough levels.

Table 13: Pharmacokinetic Parameters of HYQVIA Compared to Intravenously Administered Immune Globulin Infusion (Human), 10% (IGIV)
 |  | HYQVIA | IGIV
Number of Patients |  | 60 | 68
IgG Weekly Dose [mg/kg/week]
 | Mean (SD) | 147 (50) | 139 (55)
 | 95% CI | 134 to 160 | 126 to 153
Cmax [mg/dL]
 | Mean (SD) | 1607 (382) | 2248 (547)
 | 95% CI | 1508 to 1706 | 2116 to 2380
IgG Trough Levels [mg/dL] [N=58 for HYQVIA and N=67 for IGIV.]
 | Mean (SD) | 1077 (275) | 1095 (321)
 | 95% CI | 1004 to 1149 | 1017 to 1174
AUC/week [g*days/L] [Standardized to a 7-day interval.]
 | Mean (SD) | 91.4 (21) | 98.7 (24.3)
 | 95% CI | 85.9 to 96.8 | 92.8 to 104.5
Bioavailability [calculated based on weekly AUC; N=58 for HYQVIA.]
 | Point estimate | 93.3 | 100% (defined)
 | 90% CI | 91.4 to 95.2 | N/A
Clearance [mL/kg/day]
 | Mean (SD) | 1.6 (0.5) [Apparent clearance] | 1.4 (0.4)
 | 95% CI | 1.5 to 1.8 | 1.3 to 1.5
Terminal Half-life [days]
 | Mean (SD) | 59.3 (36.1) | 41.6 (26.9)
 | 95% CI | 50 to 68.6 | 35.1 to 48.1
Tmax [days]
 | Median | 5.0 | 0.1
 | 95% CI | 3.3 to 5.1 | 0.1 to 0.1

Figure 1* shows a mean concentration-time plot of IgG in patients 12 years and older. The concentration-time profile of HYQVIA is similar to that of intravenous administration but without the high peak. The peak to trough variation is more similar to subcutaneous administration.

Figure 1: Pharmacokinetic Comparison of Mean IgG Values for HYQVIA vs. Intravenously and Subcutaneously Administered Immune Globulin Infusion (Human), 10% [IGIV and HYQVIA data at 28-day dosing interval; IGSC data at 7-day dosing interval; IGSC dotted line shows weekly dose extrapolated over 21 additional days.]

Pediatric Population

Results from the pivotal pediatric study suggest no clinically meaningful differences across age (2 to 16 years) groups with respect to total IgG PK (AUC/week and CL/F/BW) and serum trough levels.

Chronic Inflammatory Demyelinating Polyneuropathy (CIDP)

The pharmacokinetic profile of HYQVIA was not evaluated in clinical study 1 in patients with CIDP aged 18 years and older. Serum trough levels of total IgG were assessed throughout the study 1. Trough-level data at baseline, interim visit, and end of study were presented in Table 14.

Table 14: Summary of Serum Trough Total IgG Levels (mg/dL) in Epoch 1 of Study 1
Treatment Arm | Baseline [Baseline is defined as the last non-missing value before the last pre-randomization IGIV dose.] | Interim Visit [Interim visit is defined as Epoch 1 Week 14/15/16 depending on Dosing Regimen.] | End of Epoch 1 Treatment / Early Termination
HYQVIA
N | 45 | 44 | 46
Mean (SD) | 1465.3 (323.6) | 1487.1 (348.0) | 1569.5 (450.4)
Min, Max | 966, 2230 | 755, 2510 | 855, 2880
Placebo
N | 55 | 40 | 55
Mean (SD) | 1477.6 (356.9) | 1113.4 (275.9) | 1240.8 (574.3)
Min, Max | 655, 2870 | 449, 1690 | 449, 4680
SD = Standard deviation. N = Number of patients who had a value at each time point.

13 NONCLINICAL TOXICOLOGY

13.1 Carcinogenesis, Mutagenesis, Impairment of Fertility

Immune Globulin Infusion (Human), 10%

Long-term animal studies have not been conducted to evaluate the carcinogenic potential of Immune Globulin Infusion (Human), 10% or its effect on fertility.

An in vitro mutagenicity test was performed for Immune Globulin Infusion (Human), 10%. No evidence of mutagenicity was observed.

rHuPH20

Hyaluronidases are found in most tissues of the body. Long-term animal studies to evaluate the carcinogenic or mutagenic potential of rHuPH20 have not been conducted.

No adverse effects on fertility were observed in mice, rabbits and cynomolgus monkeys exposed to antibodies that bind to rHuPH20 and species-specific hyaluronidase. Reversible infertility has been observed in male and female guinea pigs immunized to produce antibodies to hyaluronidase. However, antibodies to hyaluronidase did not influence reproduction following immunization of mice, rabbits, sheep, or cynomolgus monkeys. The effects of antibodies that bind to rHuPH20 on human fertility are unknown.

13.2 Animal Toxicology and/or Pharmacology

Developmental studies in mice demonstrated that administration of rHuPH20 did not produce teratogenicity or signs of maternal toxicity at doses up to 18 mg/kg (2.2 × 10^6 U/kg), which is 28,800 times higher than the typical monthly human dose. Maternal doses of 9 and 18 mg/kg were associated with reduced fetal weight and an increased number of fetal resorptions. No adverse effects on fetal development were observed at a maternal dose of 3 mg/kg (360,000 U/kg) in mice and 0.76 mg/kg (91,000 U/kg) in rabbits, which is 4,800 and 1,200 times higher than the typical monthly human dose.

In a peri-and post-natal reproduction study, female mice were dosed daily with rHuPH20 from implantation through lactation and weaning. There were no adverse effects on gestation, parturition, lactation and maternal behavior or on the development of the male or female offspring of the treated female mice in terms of sexual maturation, learning and memory of offspring, or their ability to produce another generation of offspring at doses up to 9 mg/kg (1.1 ×10^6 Unit/kg), which is 14,400 times higher than the typical monthly human dose.

14 CLINICAL STUDIES

14.1 Primary Immunodeficiency (PI)

A prospective, open-label, non-controlled, multicenter trial was conducted in the US to determine the efficacy, tolerability, and pharmacokinetics (PK) of HYQVIA in patients with PI. Two cohorts of patients were enrolled. Thirty-one patients had been treated intravenously for three months and then subcutaneously each week at 137% of the intravenous dose for approximately one year before transitioning to the HYQVIA trial. The remaining patients also were treated intravenously for 3 months and then immediately began treatment with HYQVIA in the trial.

One week after the last intravenous or subcutaneous infusion, each subject began subcutaneous treatment with HYQVIA. After placing the subcutaneous needle set, the rHuPH20 of HYQVIA was infused through the needle set followed within 10 minutes by the immune globulin of HYQVIA at 108% of the intravenous dose. Dosing began with a 1-week equivalent dose. One week later, a 2-week dose was administered, followed 2 weeks later with a 3-week dose. For those patients who were on a 4-week dose interval prior to entering the trial, 3 weeks later the 4-week dose was administered. This ramp-up period allowed patients to become familiar with the large volumes required for a full 3- or 4-week treatment. Subsequently, patients continued the 3- or 4-week dosing for the remainder of the trial. After 3 doses at the full volume, a serum IgG trough level was obtained for all patients and used to individually adapt the subcutaneous dose of HYQVIA to compensate for individual variation from the mean value of 108% [see Clinical Pharmacology (12.3) and Administration (2.2)]. All patients who completed the trial received a minimum of 12 infusions at this individually adapted dose. The period after the ramp-up was considered the efficacy period and used for safety and efficacy analyses.

Outcome measures included the rate of infections, adverse reactions, tolerability of the infusions of HYQVIA, number of infusion sites per month, and infusion rate. Eighty-nine patients were enrolled, 87 treated intravenously and 83 treated with HYQVIA. The majority were Caucasian (79/87, 90.8%). Median age was 35.0 years (range 4 to 78 years). Forty-four of the patients were naïve to subcutaneous treatment. Median serum IgG trough levels for the 6 months before enrollment were 1033.5 mg/dL (range: 405 to 3200 mg/dL) in subcutaneous-experienced patients and 1000 mg/dL (range: 636 to 3200 mg/dL) in the subcutaneous-naïve patients.

The 83 patients received a total of 1,359 infusions of HYQVIA during the entire trial. Of these, 1,129 were administered after the ramp-up when the patients were on a consistent interval of 3 or 4 weeks, which was predetermined to be the efficacy period for data analysis.

Median duration of treatment in the IGIV period was 91 days (range 84 to 122 days). Median duration of HYQVIA treatment during the dose ramp up period was 42 days (range 20 to 49), and during the efficacy period was 366 days (range 42 to 507 days). None of the patients withdrew due to a severe or serious local or systemic adverse reaction [see Adverse Reactions (6.1)].

There were two acute serious bacterial infections (aSBI), both of which were episodes of pneumonia treated as outpatients with oral antibiotics during the 12-month efficacy period; an additional pneumonia requiring hospitalization occurred during the ramp-up. Based on this, the annualized rate of aSBI while treated with HYQVIA was 0.025, with an upper 99% confidence limit of 0.089, which is significantly less than (p<0.0001) the rate of one infection per year.

The overall rates of infections throughout both the efficacy and extension trials are shown in Table 15. The secondary endpoints evaluated in the efficacy trial were the annual rate of all infections and other efficacy measures.

Table 15: Summary of Infections and Other Secondary Efficacy Endpoints
Annual Rate
Parameter | Mean | 95% CI
Infections per patient per year (Efficacy Trial) | 2.97 | 2.51 to 3.47
Infections per patient per year (Efficacy and Extension Trials) | 2.99 | 2.60 to 3.42
Days off school/work | 3.31 | 2.37 to 4.47
Days on antibiotics | 20.26 | 15.45 to 25.98
Unscheduled physician visits for infections | 4.78 | 3.83 to 5.88
Days in hospital due to infection | 0.037 | 0.009 to 0.095

An objective of the trial was to achieve the same number or fewer infusions with HYQVIA per month as with intravenous administration and significantly fewer than with conventional subcutaneous administration. A summary of intravenous administration compared with HYQVIA administration is presented in Table 16.

Table 16: Summary of Infusions
Parameter | Intravenous | HYQVIA
Median monthly number of infusion sites | 1.34 (1.2 to 1.7) | 1.09 (1.0 to 3.5)
Mean volume per site (mL) | 339 (75 to 800) | 292 (91 to 648)
Dose per site (g) | 33.9 (7.5 to 80.0) | 29.2 (9.1 to 64.8)
Median duration of individual infusions (hr) | 2.33 (0.92 to 6.33) | 2.08 (0.83 to 4.68)
Monthly median infusion time (hr/month) | 3.2 | 2.64
Median maximum infusion rate (mL/hr) | 246 (60 to 668) | 300 (10 to 300)
Percent (%) of infusion completed without change in rate, interruption, and discontinuation | 95.9 | 97.7

Sixteen of 83 patients (19.3%) were infused every 3 weeks and 67 (80.7%) were infused every 4 weeks. Seventy-eight of 83 (94%) patients attained the same 3- or 4-week dosing as their previous IV treatment. One decreased from 4 to 3 weeks, one from 4 to 2 weeks and one from 3 to 2 weeks. The primary reason for decreasing the interval was discomfort due to swelling.

In a separate study evaluating subcutaneous treatment with Immune Globulin Infusion (Human), 10% a median of 21.43 sites were required each month with a median monthly infusion time of 5.35 hours.

Pediatric Study

A prospective, open-label, non-controlled, multicenter trial was conducted in the US to determine the efficacy, safety, immunogenicity and pharmacokinetics (PK) of HYQVIA in pediatric patients with PI who had received IVIG or SCIG treatment before enrollment into the trial. A total of 44 patients were enrolled, and the median age of pediatric patients was 9.5 years (range: 3 to 15 years). Of the enrolled patients, 26 patients (59.1%) were male, 18 patients (40.9%) were female, and 40 patients (90.9%) were White. Most patients were not Hispanic or Latino (39 patients [88.6%]).

Pediatric patients switched to HYQVIA SC immunoglobulin treatment schedule administered at doses (volumes and treatment intervals) typical for IVIG administration. Treatment intervals and doses gradually increased in a ramp-up phase to an interval of 3 or 4 weeks. Data were analyzed when all patients completed 12 months of participation (one year of observation) in the trial. Overall, the median number of infusions per month was 1.1 (range: 1.0 to 1.5) and was comparable across the age groups. The median number of infusion sites per month was 2.2 (range: 1.1 to 2.9), with a similar median number for all age categories. There were no clinically meaningful differences in trough IgG levels across age groups.

The primary analysis for efficacy was based on the rate of aSBIs, defined as bacteremia/sepsis, bacterial meningitis, osteomyelitis/septic arthritis, bacterial pneumonia, and visceral abscess, per subject per year. Secondary analyses included the annual rate of other infections and health resource utilization outcome measures (e.g., days out of work/school/daycare).

During the 12-month trial period, the mean aSBI rate per year was 0.04 (with an upper 1-sided 99% confidence interval of 0.21, p<0.001), which met the predefined success rate of less than one aSBI per subject per year. One subject experienced two aSBIs of bacterial pneumonia, and there were no other episodes of serious bacterial infections reported in this trial. The mean rate of all infections per subject-year was 3.20, with an upper limit of the 95% CI of 4.05. The overall rate of infections per subject is consistent with results obtained in the pivotal clinical study. Pediatric patients missed a mean (95% CI) of 5.0 (2.2 to 7.9) days of work/school/daycare.

14.2 Chronic Inflammatory Demyelinating Polyneuropathy (CIDP)

Safety and efficacy of HYQVIA in adult patients with CIDP was evaluated in a randomized, placebo-controlled study (Study 1) and a single-arm, open-label, extension study (Study 2).

Study 1:

In a multicenter, randomized, placebo-controlled, phase 3 study, 132 adult patients with CIDP underwent evaluation of safety and tolerability, 122 patients underwent efficacy evaluation of HYQVIA as a maintenance therapy to prevent relapse that allowed self-infusion of a total therapeutic dose every 2 to 4 weeks. The study enrolled patients ≥18 years of age (male or female) at the time of screening who had a documented diagnosis of definite or probable CIDP as per the European Federation of Neurological Societies/Peripheral Nerve Society (EFNS/PNS) 2010 criteria. All eligible patients had responded to IgG treatment in the past (partial or complete resolution of neurological symptoms and deficits) and were on a stable dose of IGIV treatment within the dose range equivalent to a cumulative monthly dose of 0.4 to 2.4 g/kg body weight administered intravenously for at least 12 weeks before screening. The primary endpoint was the proportion of patients who experienced a relapse, defined as an increase of ≥1 point relative to the pre-SC treatment baseline score in 2 consecutive adjusted inflammatory neuropathy cause and treatment (INCAT) disability scores obtained less than seven days apart.

Overall, a total of 184 patients were screened, of which 46 (25%) were screen failures, 138 (75%) were randomized, and 132 (71.7%) received either HYQVIA (N=62) or placebo (N=70), 17 discontinued in Epoch 1, and 94 completed the study without developing a relapse in Epoch 1 and 21 rolled over to Epoch 2. All 132 treated patients were analyzed for safety and 122 patients (N= 57 for HYQVIA, N=65 for placebo) were analyzed for efficacy included in the modified intent-to-treat (mITT). The mean duration of exposure was 5.3 months in the HYQVIA group and 4.7 months in the placebo group. The mean monthly equivalent dose was 1.1g/kg. The average time to deliver the monthly HYQVIA dose was approximately 2 hrs. HYQVIA infusions were administered through 1 to 3 injection sites, and the majority of infusions (85.8%) were administered through 2 infusion sites using 12mm to 14mm needles.

The analysis of the primary endpoint demonstrated a statistically significant difference between the relapse rates in the HYQVIA group (N=57, 14.0%) compared to the placebo group (N=65, 32.3%) (p=0.0314). The treatment difference of –18.3% (two-sided 95% CI: -32.1%, -3.1%) indicated that HYQVIA demonstrated superiority over placebo in preventing relapse of CIDP.

Kaplan-Meier curves (Figure 2) demonstrated early separation between HYQVIA and placebo at approximately Week 4.

Figure 2: Kaplan-Meier Curves for Time to Relapse by Treatment Group

The effect of HYQVIA on activities of daily living was measured by the Rasch-built Overall Disability Scale (R-ODS) centile score. The least squares (LS) mean changes were -1.2 in the HYQVIA group and -6.3 in the placebo group. The LS mean treatment difference between HYQVIA and placebo was 5.1.

Study 2:

A Phase 3b, single-arm, open-label, multicenter, extension study to assess the long-term safety, tolerability, and immunogenicity of HYQVIA for maintenance therapy for CIDP. The study was open to patients who completed Study 1 without CIDP worsening or relapse. The dosing range was 0.4 g/kg to 2.4 g/kg, given in a frequency of 2-, 3-, or 4-week intervals. An interim analysis was performed, and the data included 79 patients with a range of follow-ups from 0 to 5.1 years and a total follow-up of 169 patient-years. A total of 2,590 HYQVIA infusions were administered.

The proportion of patients who developed CIDP relapse was 8.8% (5/57) during the interim study period. The 6-month relapse rate was 1.6%.

16 HOW SUPPLIED/STORAGE AND HANDLING

How Supplied

HYQVIA is supplied in a dual vial unit of two single dose vials containing the labeled amount of functionally active Immune Globulin Infusion (Human), 10% and rHuPH20. The packaging of this product is not made with natural rubber latex.

The following presentations of HYQVIA are available:

 | Immune Globulin Infusion (Human), 10% |  | rHuPH20
NDC Number | Volume | Grams Protein | Volume | Units
0944-2510-02 | 25 mL | 2.5 | 1.25 mL | 200
0944-2511-02 | 50 mL | 5.0 | 2.5 mL | 400
0944-2512-02 | 100 mL | 10.0 | 5.0 mL | 800
0944-2513-02 | 200 mL | 20.0 | 10.0 mL | 1600
0944-2514-02 | 300 mL | 30.0 | 15.0 mL | 2400

Storage and Handling

- Do not freeze.
- Keep the vials in the carton in order to protect from light.
- Refrigeration: 2° to 8°C [36° to 46°F] for up to 36 months.
- Room Temperature: up to 25°C [77°F] for up to 3 months during the first 24 months from the date of manufacturing (Mfg date) printed on the carton.
- HYQVIA must be used within 3 months after removal to room temperature but within the expiration date on the carton and vial label.
- Do not return HYQVIA to the refrigerator after it has been stored at room temperature.

17 PATIENT COUNSELING INFORMATION

Advise the patient to read the FDA-approved patient labeling (Patient Information).

Inform patients to immediately report the following signs and symptoms to their healthcare professional:

- Acute respiratory distress, wheezing, swelling of the airway or severe hives or itching [see Warnings and Precautions (5.1)].
- Instruct patients to immediately report symptoms of thrombosis. These symptoms may include pain and/or swelling of an arm or leg with warmth over the affected area, discoloration of an arm or leg, unexplained shortness of breath, chest pain or discomfort that worsens on deep breathing, unexplained rapid pulse, numbness or weakness on one side of the body [see Warnings and Precautions (5.2)].
- Advise patients that antibodies against Recombinant Human Hyaluronidase (rHuPH20) can develop. The potential exists for such antibodies to cross-react with endogenous Hyaluronidase (PH20), which is known to be expressed in the adult male reproductive tract. The clinical significance of these antibodies is unknown [see Warnings and Precautions (5.3)].
- Severe headache, neck stiffness, drowsiness, fever, sensitivity to light, painful eye movements, nausea, and vomiting which suggest aseptic meningitis syndrome [see Warnings and Precautions (5.4)].
- Increased heart rate, fatigue, yellowing of the skin or eyes, and dark-colored urine may suggest hemolysis [see Warnings and Precautions (5.5)].
- Decreased urine output, sudden weight gain, fluid retention/edema, and/or shortness of breath may suggest kidney problems [see Warnings and Precautions (5.6)].
- Trouble breathing, chest pain, blue lips or extremities, or fever that can occur 1 to 6 hours after an infusion of HYQVIA, may suggest TRALI [see Warnings and Precautions (5.8)].
- Inform patients that HYQVIA is made from human plasma and may contain infectious agents that can cause disease (e.g., viruses and, theoretically, the vCJD agent). Patients should report any symptoms that concern them which might be caused by virus infections [see Warnings and Precautions (5.9)].
- Inform patients that HYQVIA can interfere with their immune response to live viral vaccines such as measles, mumps, rubella, and varicella, and instruct patients to notify their healthcare professional of this potential interaction when they are receiving vaccinations [see Drug Interactions (7)].

Self-administration – If self-administration is deemed appropriate by the physician, give clear instructions and training on how to administer HYQVIA. Document their ability to independently administer HYQVIA.

- Ensure the patient understands the importance of following regularly scheduled infusions to maintain appropriate steady IgG levels.
- Instruct the patient to keep a treatment infusion log. This infusion log should include information about each infusion such as, the lot number(s), infusion site location, the time, date, dose, and any reactions.
- Inform the patient that due to the volume that can be infused, swelling is common with HYQVIA. Mild to moderate local infusion-site reactions (e.g., swelling and redness) are common side effects of facilitated subcutaneous treatment with HYQVIA. Instruct the patient to contact their healthcare professional if a local reaction increases in severity or persists for more than a few days.
- Instruct the patient on the importance of following the directions for the pump for infusion of the Immune Globulin Infusion (Human), 10% of HYQVIA.

Takeda Pharmaceuticals U.S.A., Inc.
Cambridge, MA 02142

U.S. License No. 1898

HYQVIA is a registered trademark of Baxalta Incorporated.

Takeda and are registered trademarks of Takeda Pharmaceutical Company Limited.

©2024 Takeda Pharmaceutical Company Limited. All rights reserved.

Patented: see www.takeda.com/en-us/patents

HYQ353

Patient Information
HYQVIA®
Immune Globulin Infusion (Human) 10%
With Recombinant Human Hyaluronidase (rHuPH20)
For Subcutaneous Administration

The following summarizes important information about HYQVIA (pronounced Hi-Q-via). Please read it carefully before using this medicine. This information does not take the place of talking with your healthcare professional, and it does not include all of the important information about HYQVIA. If you have any questions after reading this, ask your healthcare professional.

What is the most important information that I should know about HYQVIA?

- HYQVIA can cause blood clots.
- Call your healthcare professional if you have pain, swelling, warmth, redness, or a lump in your legs or arms, other than at the infusion site(s), unexplained shortness of breath, chest pain or discomfort that worsens on deep breathing, unexplained rapid pulse, numbness or weakness on one side of the body.
- Your healthcare professional may perform blood tests regularly to check your IgG level.
- Do not infuse HYQVIA into or around an infected or red swollen area because it can cause infection to spread.

What should I tell my healthcare professional before I start using HYQVIA?

Before starting HYQVIA, tell your healthcare professional if you:

- Have or had any kidney, liver, or heart problems or history of blood clots because HYQVIA can make these problems worse.
- Have IgA deficiency or a history of severe allergic reactions to IgG or other blood products.
- Are pregnant, trying to become pregnant or are breast feeding.

What is HYQVIA?

HYQVIA is a liquid medicine containing immune globulin and Recombinant Human Hyaluronidase. HYQVIA contains IgG antibodies, collected from human plasma donated by healthy people.

- The antibodies help your body to fight off bacterial and viral infections. People who have CIDP are believed to have an autoimmune disease in which the body's immune system targets the nerves, leading to muscle weakness and numbness, usually in the arms and legs. IgG is thought to reduce the damage to the nerve and assist in defending the nerve from harm.
- The hyaluronidase is found in your body naturally. It’s the first part of your two-part infusion. It temporarily opens the space under your skin (the subcutaneous space), allowing a larger amount of IgG to reach your subcutaneous tissue and be absorbed into your bloodstream.

Who should not take HYQVIA?

- Do not take HYQVIA if you: Are allergic to IgG, hyaluronidase, other blood products, or any ingredient in HYQVIA.

How should I take HYQVIA?

- HYQVIA is infused under the skin (subcutaneously) up to once every 4 weeks.
- You can get HYQVIA at your healthcare professional’s office, clinic, or hospital.
- You can use HYQVIA at home. You and your healthcare professional will decide if home self-infusion is right for you.

What are the possible or reasonably likely side effects of HYQVIA?

After HYQVIA infusion a temporary, soft swelling may occur around the infusion site, which may last 1 to 3 days, due to the volume of fluid infused.

The following local reactions may occur at the site of infusion and generally go away in a few hours. Local reactions are less likely after the first few infusions.

- Mild or moderate pain
- Redness
- Swelling
- Itching

The most common side effects of HYQVIA are:

- Headache
- Vomiting
- Fatigue
- Nausea
- Fever
- Itching
- Redness
- Abdominal pain
- Back pain
- Pain in extremity

Antibodies to the hyaluronidase component of HYQVIA were formed in some patients taking HYQVIA. It is not known if there is any long-term effect. In theory, these antibodies could react with your body’s own PH20. PH20 is present in the male reproductive tract. So far, these antibodies have not been associated with increased or new side-effects.

Call your healthcare professional or go to your emergency department right away if you get:

- Hives, swelling in the mouth or throat, itching, trouble breathing, wheezing, fainting or dizziness. These could be signs of a serious allergic reaction.
- Bad headache with nausea, vomiting, stiff neck, fever, and sensitivity to light. These could be signs of swelling in your brain.
- Reduced urination, sudden weight gain, or swelling in your legs. These could be signs of a kidney problem.
- Pain, swelling, warmth, redness, or a lump in your legs or arms, other than at the infusion site(s). These could be signs of a blood clot.
- Brown or red urine, fast heart rate, yellow skin or eyes. These could be signs of a liver or blood problem.
- Chest pain or trouble breathing, blue lips or extremities. These could be signs of a lung problem.

These are not all of the possible side effects for HYQVIA. You can ask your healthcare professional for information that is provided to healthcare professionals. Talk to your healthcare professional about any side effects that bother you or that don’t go away.

How do I store HYQVIA?

Store HYQVIA refrigerated or at room temperature.

- You can store HYQVIA in the refrigerator (36° to 46°F [2° to 8°C]) for up to 36 months.
- You can store HYQVIA at room temperature (up to 77°F [25°C]) for up to 3 months during the first 24 months from the date of manufacturing (Mfg Date) printed on the carton.
- Do not return HYQVIA to the refrigerator if you take it out to room temperature.

Check the expiration date on the carton and vial label. Do not use HYQVIA after the expiration date.

Do not freeze.

Protect from light. You can use the original HYQVIA containers to protect it from light.

Resources at Takeda Available to the Patients

For more information on patient resources and education, please visit www.immunedisease.com.

Detailed Instructions for Administration

Do not use HYQVIA at home until you get instructions and training from your healthcare professional.

There are two ways to administer HYQVIA. Refer to the appropriate Instructions For Use (IFU). Your healthcare professional will decide which administration system is right for you. You will take the hyaluronidase first. Then, within 10 minutes, you will take the immune globulin through an infusion pump.

Prepare HYQVIA vial(s):

- Remove HYQVIA from the box. Allow vials to reach room temperature. This may take up to 60 minutes or longer.
- Do not apply heat or place in microwave.
- Do not shake the vials.

To administer HYQVIA using Vial Access Devices (VAD)

Refer to the Instructions For Use (IFU) provided with the Vial Access Devices. VAD can be used to administer HYQVIA in adult patients only.

To administer HYQVIA using a needle or needle-less transfer device

Refer to the instructions below.

1. Check the vials:
2. Do not use after expiration date.
3. Do not use if the purple protective cap is missing or broken.
4. Look at the color:
  - The Recombinant Human Hyaluronidase (HY) should be clear and colorless.
  - The Immune Globulin Infusion (Human), 10% (IG) should be clear and colorless or pale yellow.
  - If either liquid is cloudy or has particles, do not use.

2. Prepare for Infusion:
2. Gather all supplies:
  Items include: dual vial unit(s) of HYQVIA, infusion supplies: subcutaneous needle set, solution container (bag or syringe), sterile clear bandage and tape, pump tubing, transfer devices, syringe(s), gauze, tape, sharps container, infusion pump, infusion log and other supplies as needed.
3. Clean work area
4. Program the infusion pump according to prescribed infusion rates and manufacturer’s instructions.
5. Wash hands thoroughly.
6. Open supplies as shown by your healthcare professional.
7. If your HYQVIA vials are pooled together by your pharmacist, skip to step 5.

3. Prepare the Hyaluronidase (Labeled as “HY”):
2. Prior to use, take off the purple protective cap(s) and make sure the blue vial caps are removed. If not, manually remove the blue caps.
3. Wipe each of the HY vials (top of vial) with an alcohol wipe and allow to dry.
4. Remove sterile syringe from package and attach to a sterile needle/needle-less transfer device. A sterile needle or needle-less transfer device [(18-22) gauge sterile needle] may be used for all vial sizes.
5. Pull back on plunger of the syringe to fill the syringe with air equal to the amount in the HY vial.
6. Position the sharp tip of the needle/needle-less transfer device over the center of the vial stopper and insert it at a 90-degree angle.
7. Inject air into the vial and withdraw the full contents of the HY vial(s) into a syringe.
8. Repeat the above steps for each additional HY vial using the same syringe, if possible.
9. Remove the syringe from the needle/needle-less transfer device.
10. Point the syringe tip up and push the plunger of the syringe to remove the air
11. If using the push method to deliver “HY”:
  - Attach the syringe filled with recombinant human hyaluronidase to the needle set
  - Push the plunger of smaller syringe to remove the air and fill the needle set up to the needle wings with the recombinant human hyaluronidase.
12. If using the pump method to deliver “HY”:
  - Clean the upper port of the pump administration tubing with alcohol swab and allow to dry for 30 seconds.
  - Attach the syringe filled with recombinant human hyaluronidase “HY” to the upper port of pump administration tubing and attach the needle set to the opposite end.
  - Close the clamp of lower port close to the needle set.
  - Push the plunger of syringe (size may vary due to a larger volume) to remove the air and fill the pump administration tubing to the spike.
  - Close the clamp above the upper port and open the clamps on the lower port and needle set. Fill up to the needle wings with the recombinant human hyaluronidase.

4. Prepare the immune globulin (Labeled as “IG”):
2. Wipe each stopper with a sterile alcohol wipe and allow to dry.
3. Transfer the vial(s) labeled IG into either syringe(s) or an infusion bag or as shown by your healthcare professional:
  - If using syringe(s)
  − Attach a sterile syringe to a vented spike.
  − Insert the vented spike into the center of the IG vials.
  − Turn the vial upside down and pull back on the plunger to pull the IG into the syringe(s).
  − Repeat these steps, if using multiple vials to achieve the desired dose.
  − If using a sterile needle, attach a sterile syringe to the sterile needle and pull back the plunger of syringe to fill with air which should equal amount of the liquid you will be taking from the vial. Insert the needle into the center of the stopper, and inject air in. Pull back on the plunger to withdraw the desired volume.
  - If using an infusion bag:
  − Insert the vented spike into the center of each IG vial. Open the vent.
  − Turn the vial upside down and fill the bag with the IG. Repeat this step, if using multiple vials to achieve the desired dose.
  − Remove the filling tube(s) of the bag and place a sterile cap over the open end of the bag and close the clamp on bag.
  − Insert the spike of the administration pump tubing into the bag and fill as directed by your healthcare professional.

5. Prepare the infusion site:
  - Choose an infusion site(s) in either the middle or upper abdomen or thigh.
  - Avoid: bony areas, visible blood vessels, scars and any areas of inflammation (irritation) or infection.
  - Select sites on the opposite sides of the body if instructed to infuse in two sites.
  - If using three sites, the sites should be 10 cm apart.
  - Rotate sites by choosing opposite sides of the body between future infusions.
  - Wipe the infusion site(s) with a sterile alcohol wipe beginning at the center of each infusion site and moving outward in a circular motion. Allow the infusion site(s) to dry (at least 30 seconds).

6. Insert and secure the 24-gauge subcutaneous needle:
2. Remove the needle cover. Firmly grasp and pinch at least 1 inch of skin between two fingers.
3. Insert needle with a rapid motion straight into the skin at a 90-degree angle. Tape needle in place with sterile tape.
4. Repeat these steps if you have a second or a third infusion site.
5. Open the clamp on the needle set.
6. If using the push method:
  - Check for proper needle placement by pulling back on the syringe plunger to check for blood return in the tubing of the needle set.
7. If using the pump method:
  - Close the clamp above the lower port of the pump tubing.
  - Clean the lower port with an alcohol swab and allow to dry, for at least 30 seconds.
  - Attach a 5 mL syringe to the lower port of the pump tubing.
  - Pull back gently on the syringe plunger.
8. If blood is seen in the tubing, remove and discard the subcutaneous needle and repeat steps 3, 5, and 6 with a new subcutaneous needle and infusion site.
9. Secure the needle set in place by applying a sterile protective dressing over the site. If more than one site is used, repeat the steps.

7. Administer the hyaluronidase (Labeled as “HY”):
2. Divide the contents equally between sites, if more than one site is used.
3. If using the push method to deliver “HY”:
  - Slowly push the plunger of the smaller syringe with the recombinant human hyaluronidase at an initial rate per infusion site to approximately 1 to 2 mL per minute and increase as tolerated.
  - Attach the pump tubing or syringe filled with the IG to the same needle set.
4. If using the pump method to deliver “HY”:
  - If using a pump, prepare the pump to infuse the recombinant human hyaluronidase at an initial rate per infusion site of 60 to 120 mL/hour/site and increase as tolerated. Turn on the pump.
  - Remove the syringe from pump administration tubing, after infusing all of the content of the syringe.
  - Open the clamp on the upper port of the pump administration tubing to administer the IG to the same needle set.

8. Administer the immune globulin (Labeled as “IG”):

Within 10 minutes of completing the infusion of the HY, start the pump to administer the IG.

- Flush infusion tubing up to the needle wings with normal saline or Dextrose 5% in water (D5W) at the end of infusion, if directed by your healthcare professional.

9. Remove subcutaneous needle(s) from the infusion site(s):
2. Remove the needle set by loosening the tape on all edges.
3. Pull the needle wings straight up and out.
4. Gently press a small piece of gauze over the needle site and cover with a dressing.
5. Throw away the needle(s) into the sharps container.

10. Record the infusion:
2. Remove the peel-off label from HYQVIA vial(s), which has the product lot number and expiration date, and place the label in your treatment record/ infusion log.
3. Write down the date, time, dose, site(s) of infusion (to assist in rotating sites) and any reactions after each infusion.
4. Throw away the disposable supplies, vials, and unused product as recommended by your healthcare professional.

Takeda Pharmaceuticals U.S.A., Inc.
Cambridge, MA 02142

U.S. License No. 1898

HYQVIA is a registered trademark of Baxalta Incorporated.

Takeda and are registered trademarks of Takeda Pharmaceutical Company Limited.

©2024 Takeda Pharmaceutical Company Limited. All rights reserved.

Patented: see www.takeda.com/en-us/patents

Revised Date: 7/2025

HYQ353

PRINCIPAL DISPLAY PANEL - 2.5 g/25 mL Vial Label

Immune Globulin Infusion (Human), 10%

Component of HYQVIA®

Single-Dose Vial

Rx Only

Takeda Pharmaceuticals U.S.A., Inc.
Cambridge, MA 02142
U.S. License No. 1898

Infuse 2nd

2.5 g/
25 mL

IG

LE-07-64433

Takeda

PRINCIPAL DISPLAY PANEL - 1.25 mL Vial Label

Recombinant Human Hyaluronidase

Component of HYQVIA®

Single-Dose Vial

Rx Only

Takeda Pharmaceuticals U.S.A., Inc.
Cambridge, MA 02142

Infuse 1st

HY

1.25 mL
160 units per mL

Takeda

PRINCIPAL DISPLAY PANEL - 2.5 g/25 mL Kit Carton

NDC 0944-2510-02

Immune Globulin Infusion (Human), 10%
with Recombinant Human Hyaluronidase
HYQVIA®

For Subcutaneous Administration Only.

Single-dose dual vial unit

Directions for use:

Read the enclosed Package Insert.
No preservative

Rx Only

2.5 g/
25 mL

Takeda

PRINCIPAL DISPLAY PANEL - 5 g/50 mL Vial Label

Immune Globulin Infusion (Human), 10%

Component of HYQVIA®

Single-Dose Vial

Rx Only

Takeda Pharmaceuticals U.S.A., Inc.
Cambridge, MA 02142
U.S. License No. 1898

Infuse 2nd

5 g/
50 mL

IG

LE-07-64435

Takeda

PRINCIPAL DISPLAY PANEL - 2.5 mL Vial Label

Recombinant Human Hyaluronidase

Component of HYQVIA®

Single-Dose Vial

Rx Only

Takeda Pharmaceuticals U.S.A., Inc.
Cambridge, MA 02142

Infuse 1st

HY

2.5 mL
160 units per mL

Takeda

PRINCIPAL DISPLAY PANEL - 5 g/50 mL Kit Carton

NDC 0944-2511-02

Immune Globulin Infusion (Human), 10%
with Recombinant Human Hyaluronidase
HYQVIA®

For Subcutaneous Administration Only.

Single-dose dual vial unit

Directions for use:

Read the enclosed Package Insert.
No preservative

Rx Only

5 g/
50 mL

Takeda

PRINCIPAL DISPLAY PANEL - 10 g/100 mL Vial Label

Immune Globulin Infusion (Human), 10%

Component of HYQVIA®

Single-Dose Vial

Rx Only

Takeda Pharmaceuticals U.S.A., Inc.
Cambridge, MA 02142
U.S. License No. 1898

Infuse 2nd

10 g/
100 mL

IG

LE-07-64437

Takeda

PRINCIPAL DISPLAY PANEL - 5 mL Vial Label

Recombinant Human Hyaluronidase

Component of HYQVIA®

Single-Dose Vial

Rx Only

Takeda Pharmaceuticals U.S.A., Inc.
Cambridge, MA 02142

Infuse 1st

5 mL
160 units per mL

HY

Takeda

PRINCIPAL DISPLAY PANEL - 10 g/100 mL Kit Carton

NDC 0944-2512-02

Immune Globulin Infusion (Human), 10%
with Recombinant Human Hyaluronidase
HYQVIA®

For Subcutaneous Administration Only.

Single-dose dual vial unit

Directions for use:
Read the enclosed Package Insert.

No preservative

Rx Only

10 g/
100 mL

Takeda

PRINCIPAL DISPLAY PANEL - 20 g/200 mL Vial Label

Immune Globulin Infusion (Human), 10%

Component of HYQVIA®

Single-Dose Vial

Rx Only

Takeda Pharmaceuticals U.S.A., Inc.
Cambridge, MA 02142
U.S. License No. 1898

Infuse 2nd

20 g/
200 mL

IG

LE-07-64439

Takeda

PRINCIPAL DISPLAY PANEL - 10 mL Vial Label

Recombinant Human Hyaluronidase

Component of HYQVIA®

Single-Dose Vial

Rx Only

Takeda Pharmaceuticals U.S.A., Inc.
Cambridge, MA 02142

Infuse 1st

HY

10 mL
160 units per mL

LE-07-62670

Takeda

PRINCIPAL DISPLAY PANEL - 20 g/200 mL Kit Carton

NDC 0944-2513-02

Immune Globulin Infusion (Human), 10%
with Recombinant Human Hyaluronidase
HYQVIA®

For Subcutaneous Administration Only.

Single-dose dual vial unit

Directions for use: Read the enclosed Package Insert.

No preservative

Rx Only

20 g/
200 mL

Takeda

PRINCIPAL DISPLAY PANEL - 30 g/300 mL Vial Label

Immune Globulin Infusion (Human), 10%

Component of HYQVIA®

Single-Dose Vial

Rx Only

Takeda Pharmaceuticals U.S.A., Inc.
Cambridge, MA 02142
U.S. License No. 1898

Infuse 2nd

30 g/
300 mL

IG

LE-07-64441

Takeda

PRINCIPAL DISPLAY PANEL - 15 mL Vial Label

Recombinant Human Hyaluronidase

Component of HYQVIA®

Single-Dose Vial

Rx Only

Takeda Pharmaceuticals U.S.A., Inc.
Cambridge, MA 02142

Infuse 1st

HY

15 mL
160 units per mL

LE-07-62673

Takeda

PRINCIPAL DISPLAY PANEL - 30 g/300 mL Kit Carton

NDC 0944-2514-02

Immune Globulin Infusion (Human), 10%
with Recombinant Human Hyaluronidase
HYQVIA®

For Subcutaneous Administration Only.

Single-dose dual vial unit

Directions for use: Read the enclosed Package Insert.

No preservative

Rx Only

30 g/
300 mL

Takeda